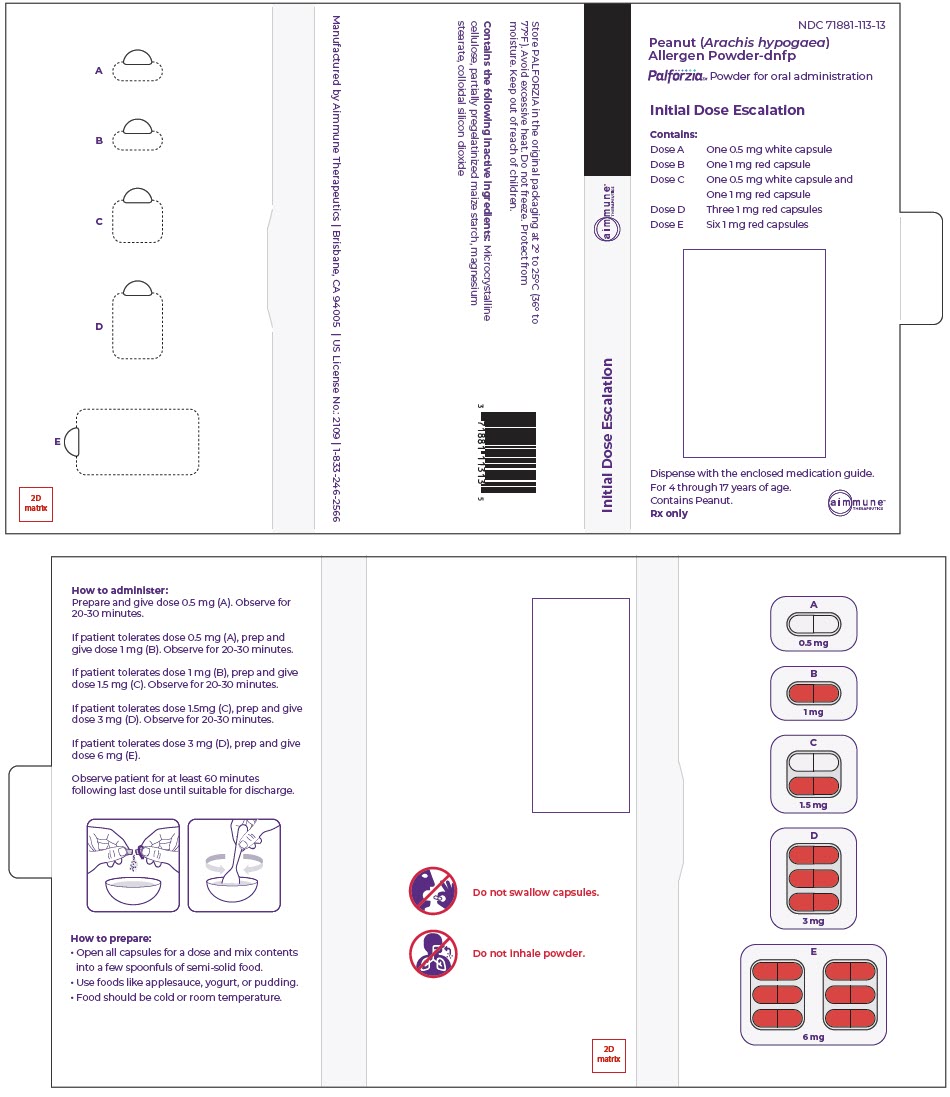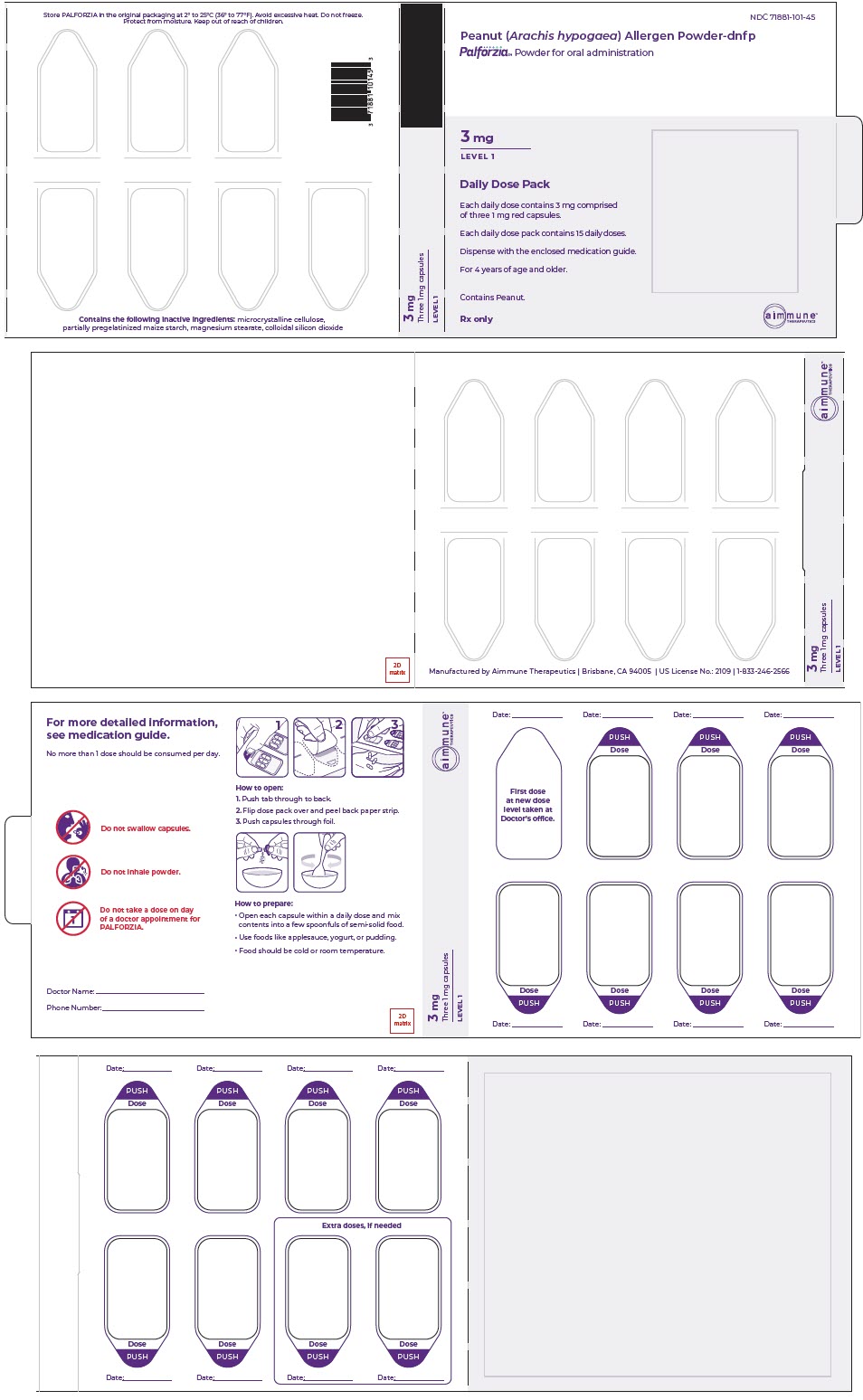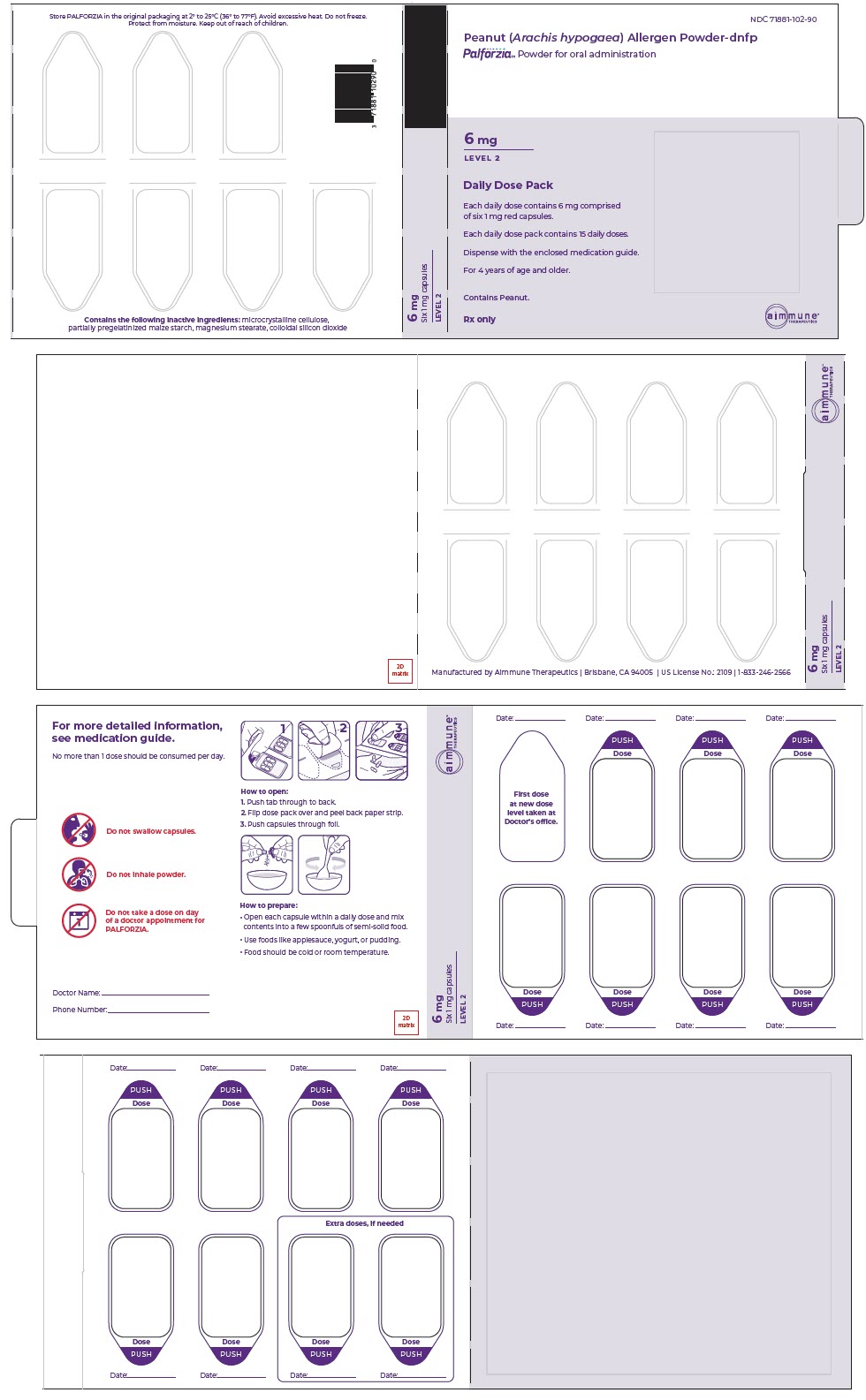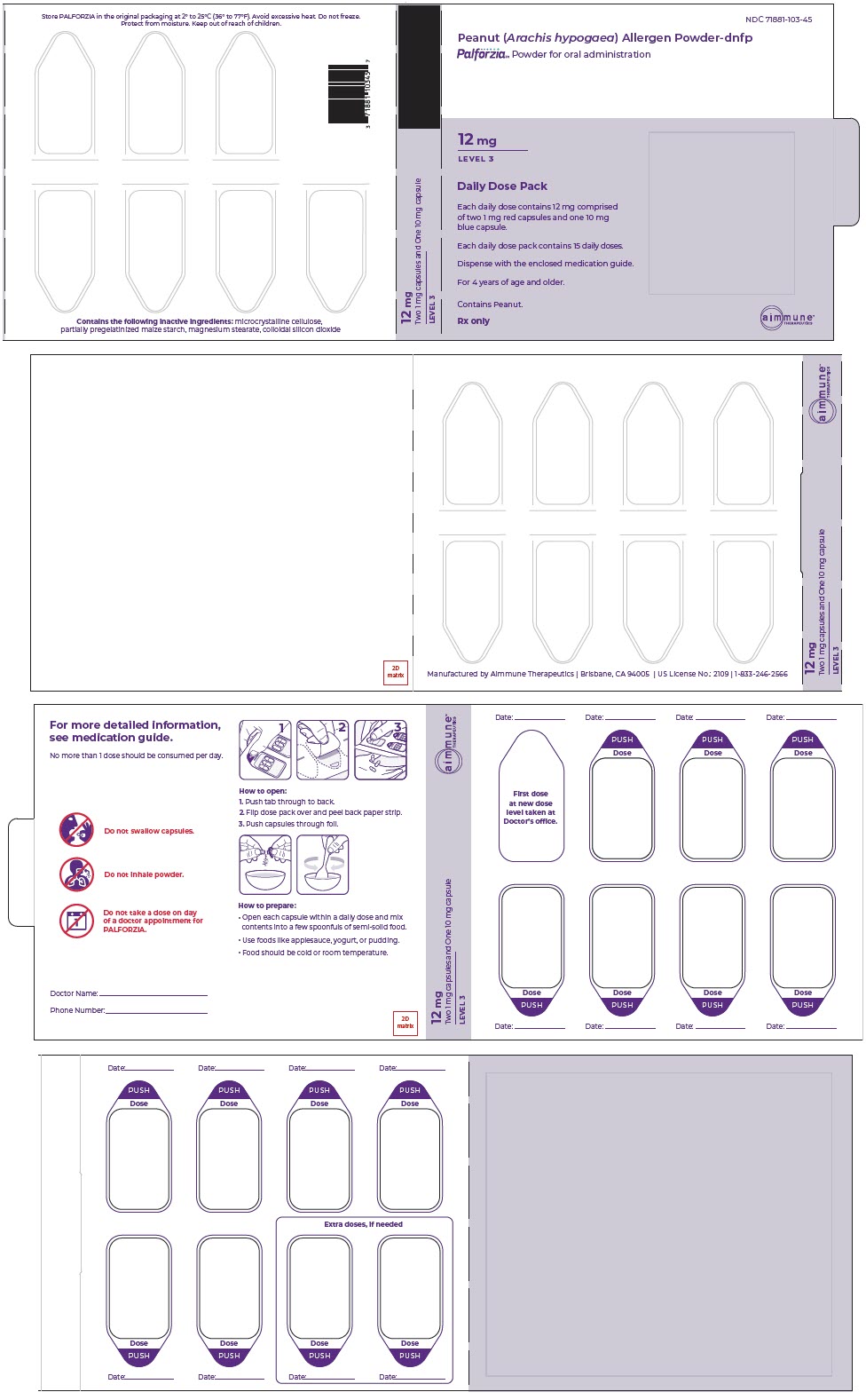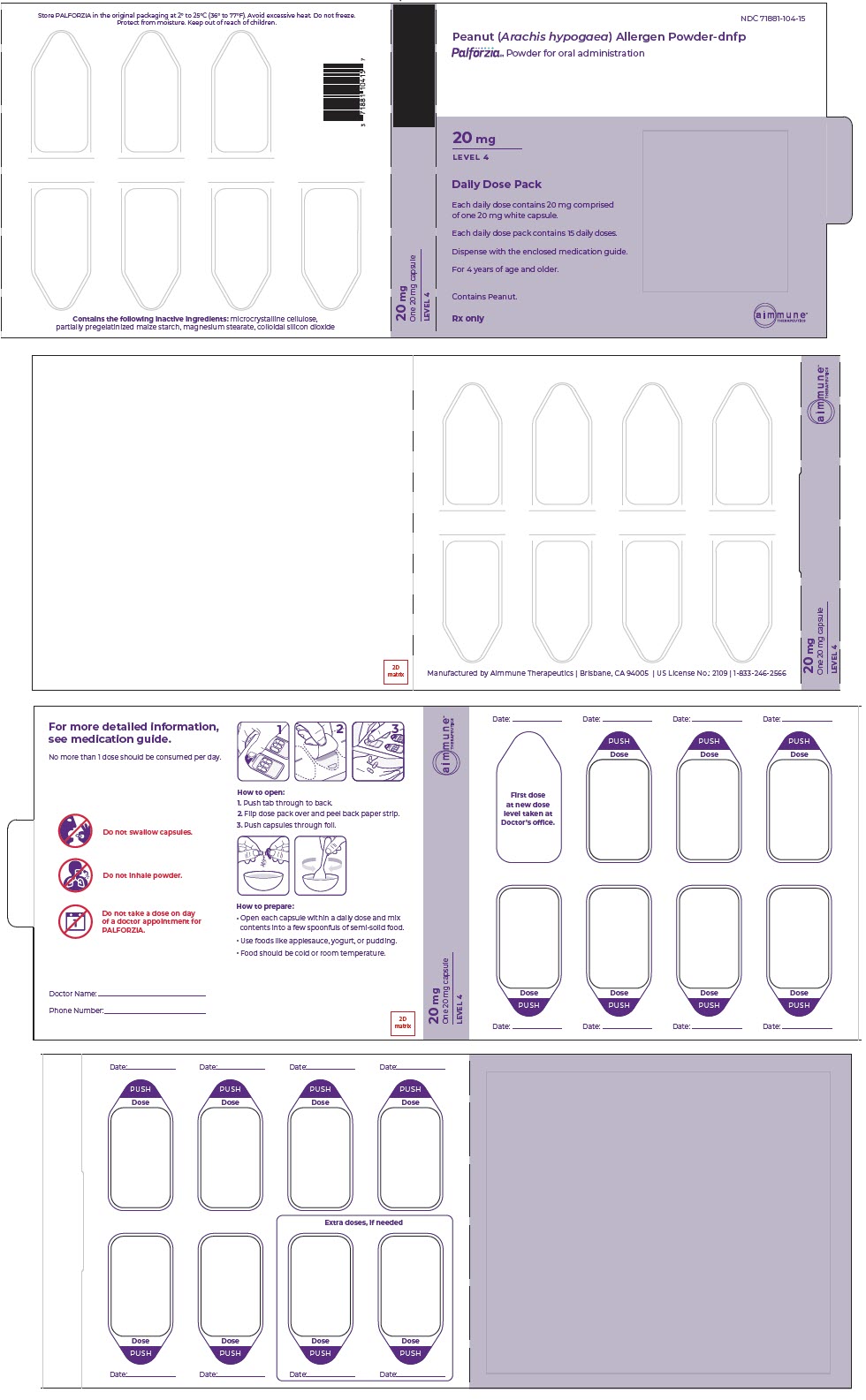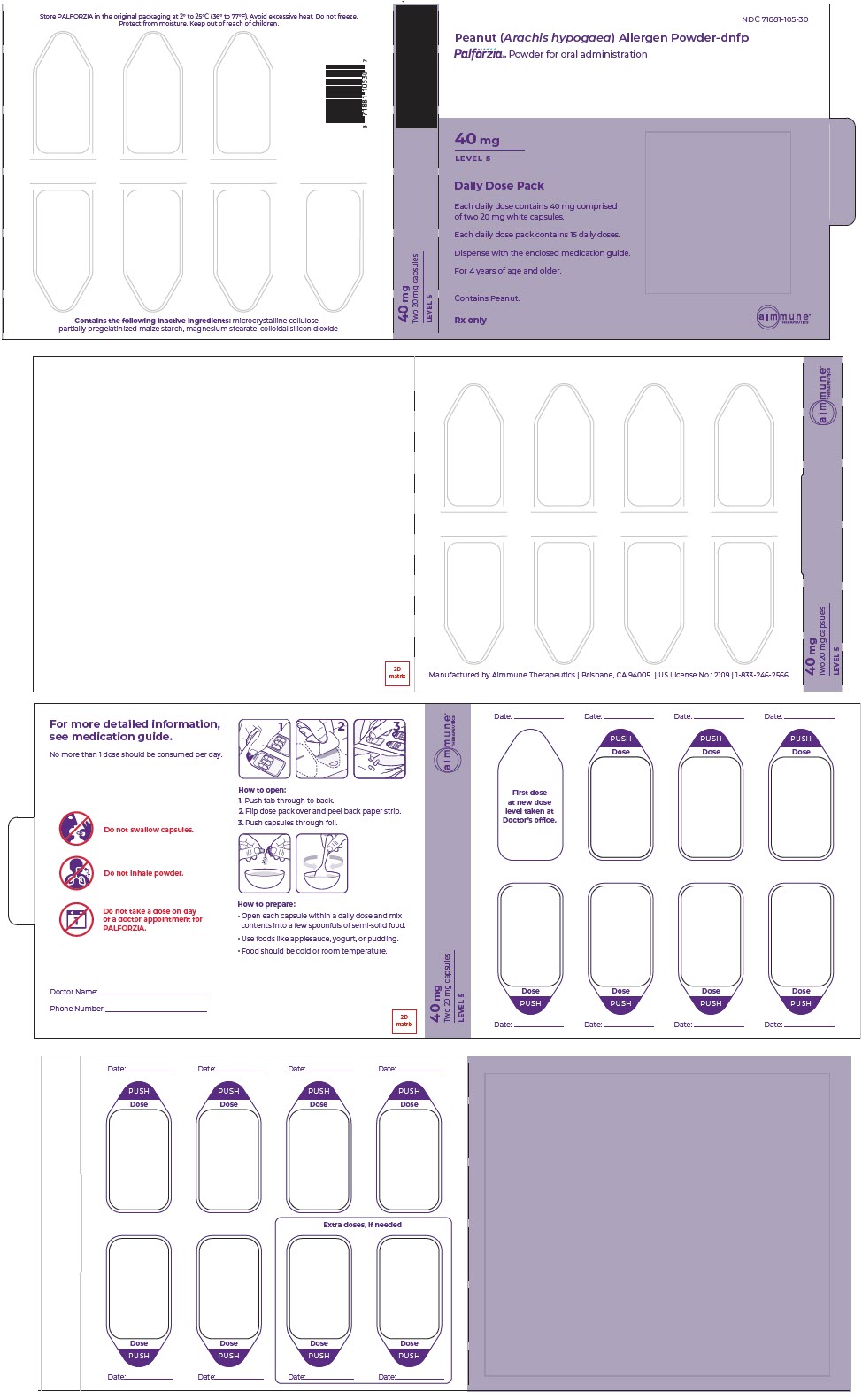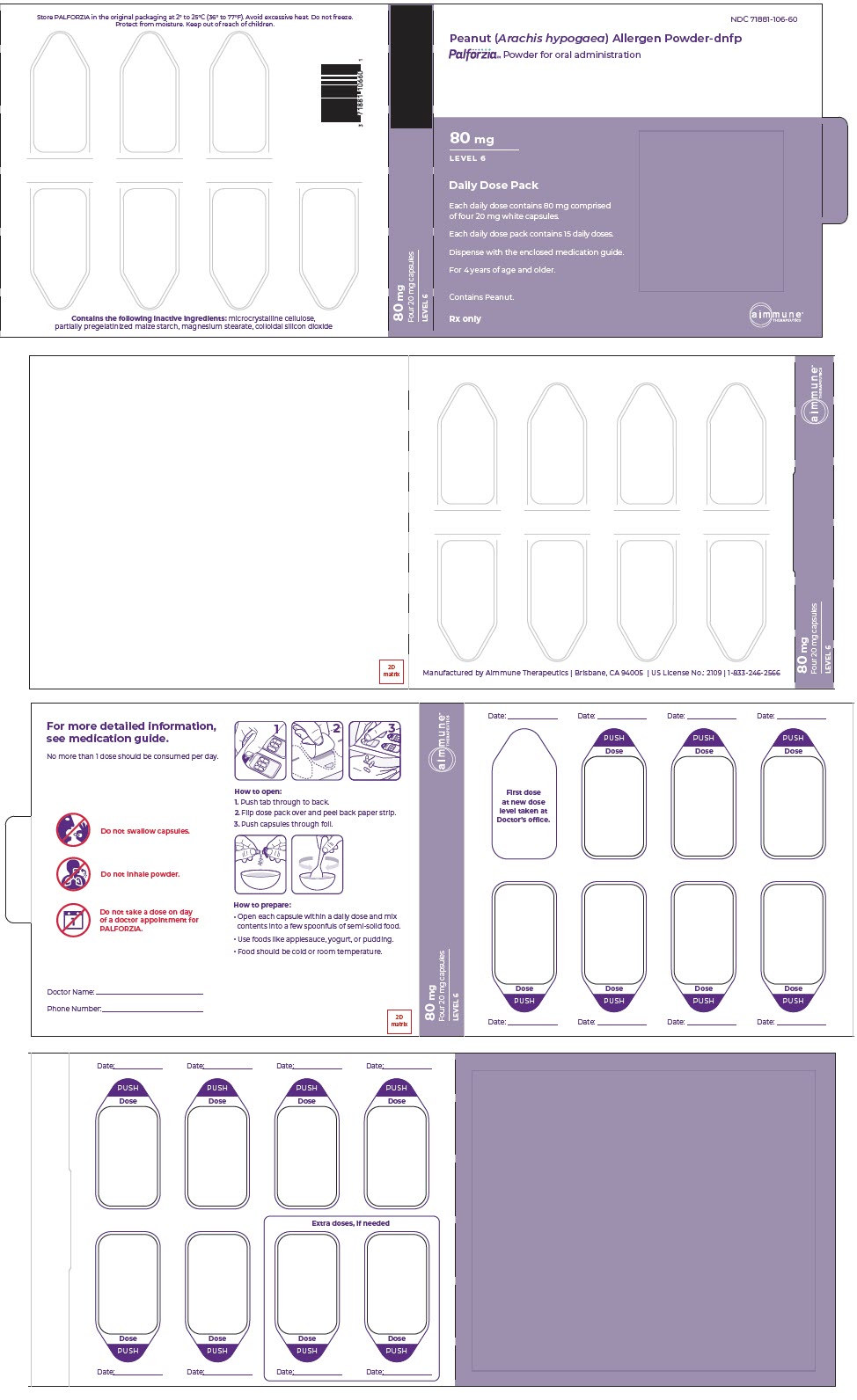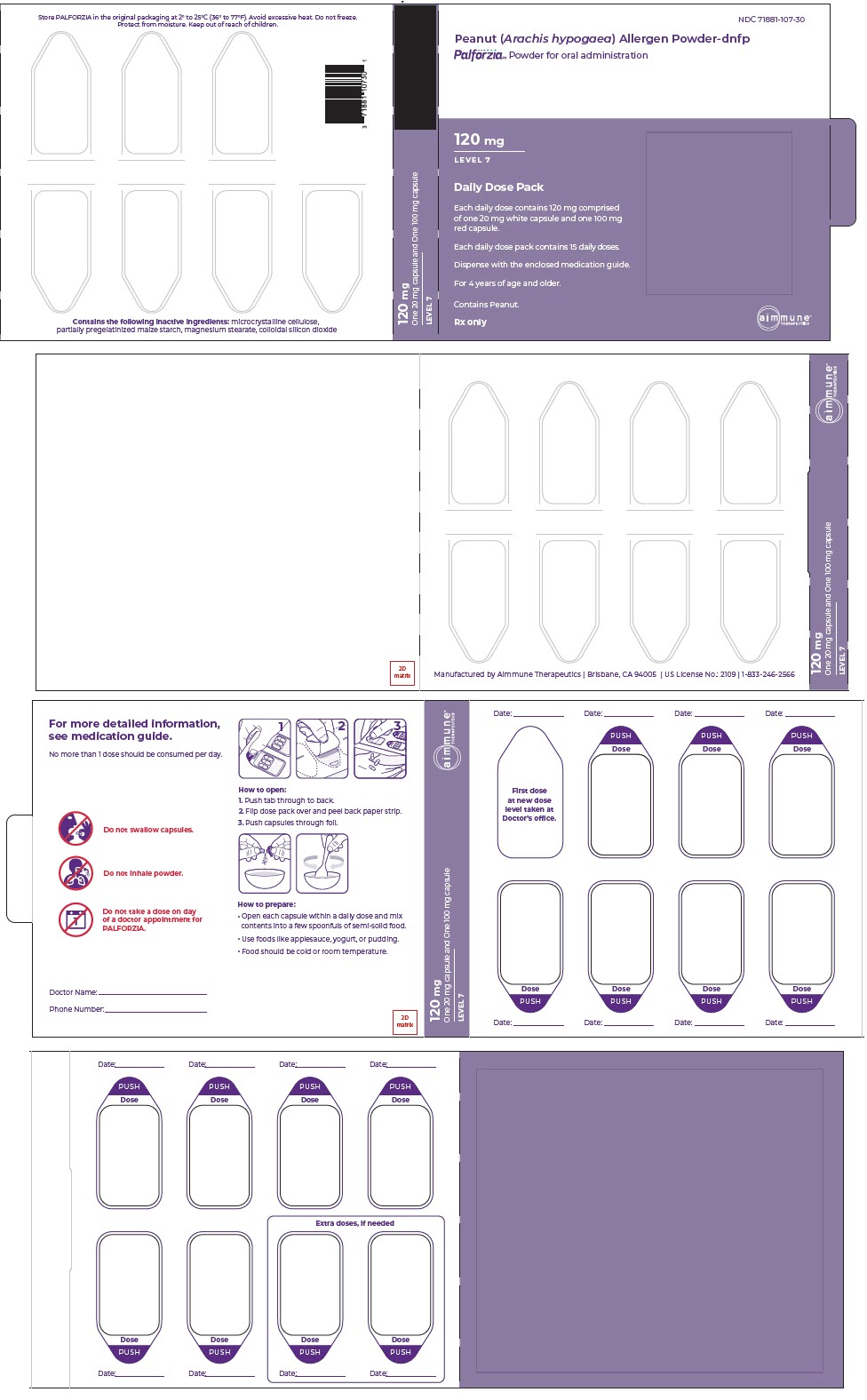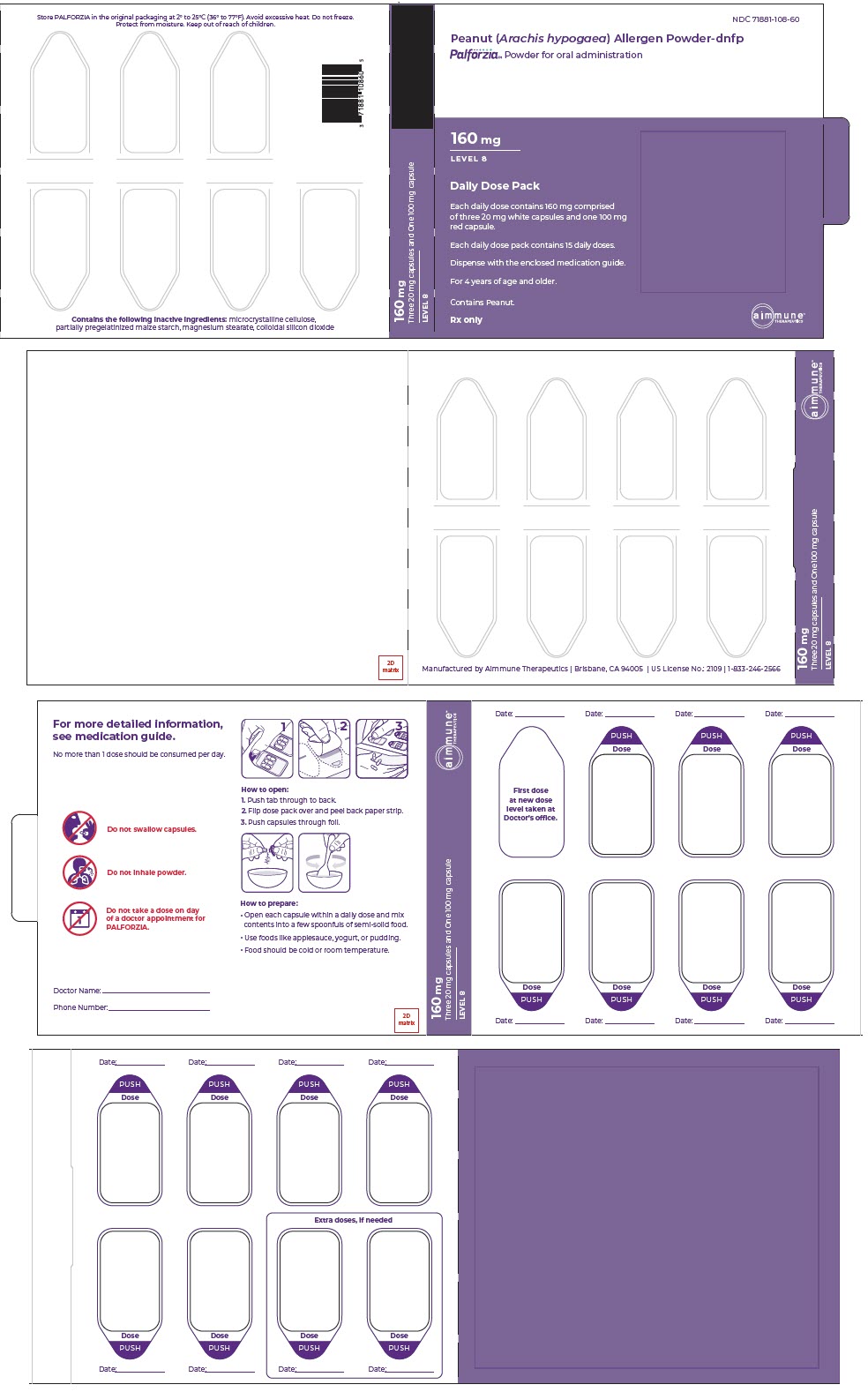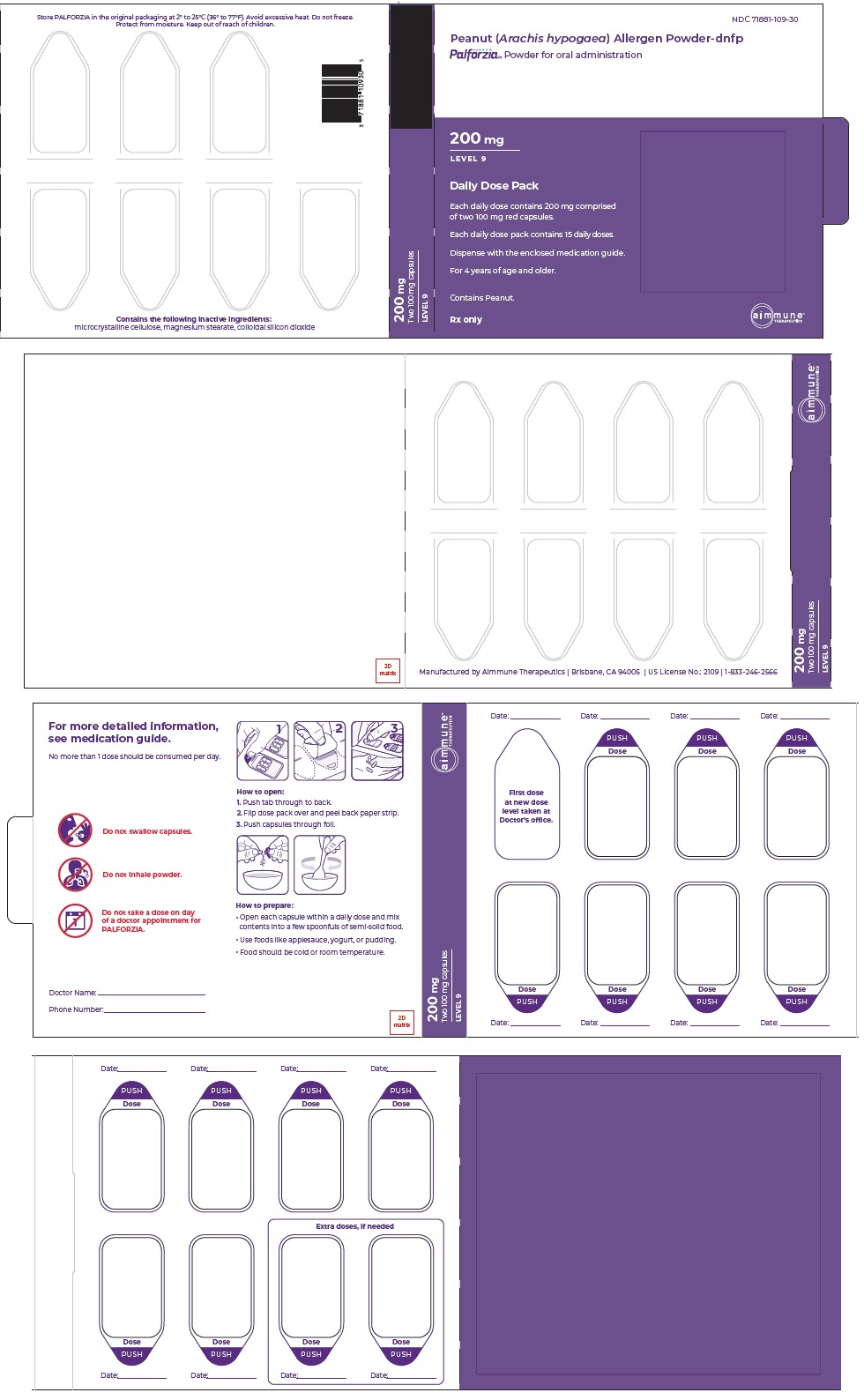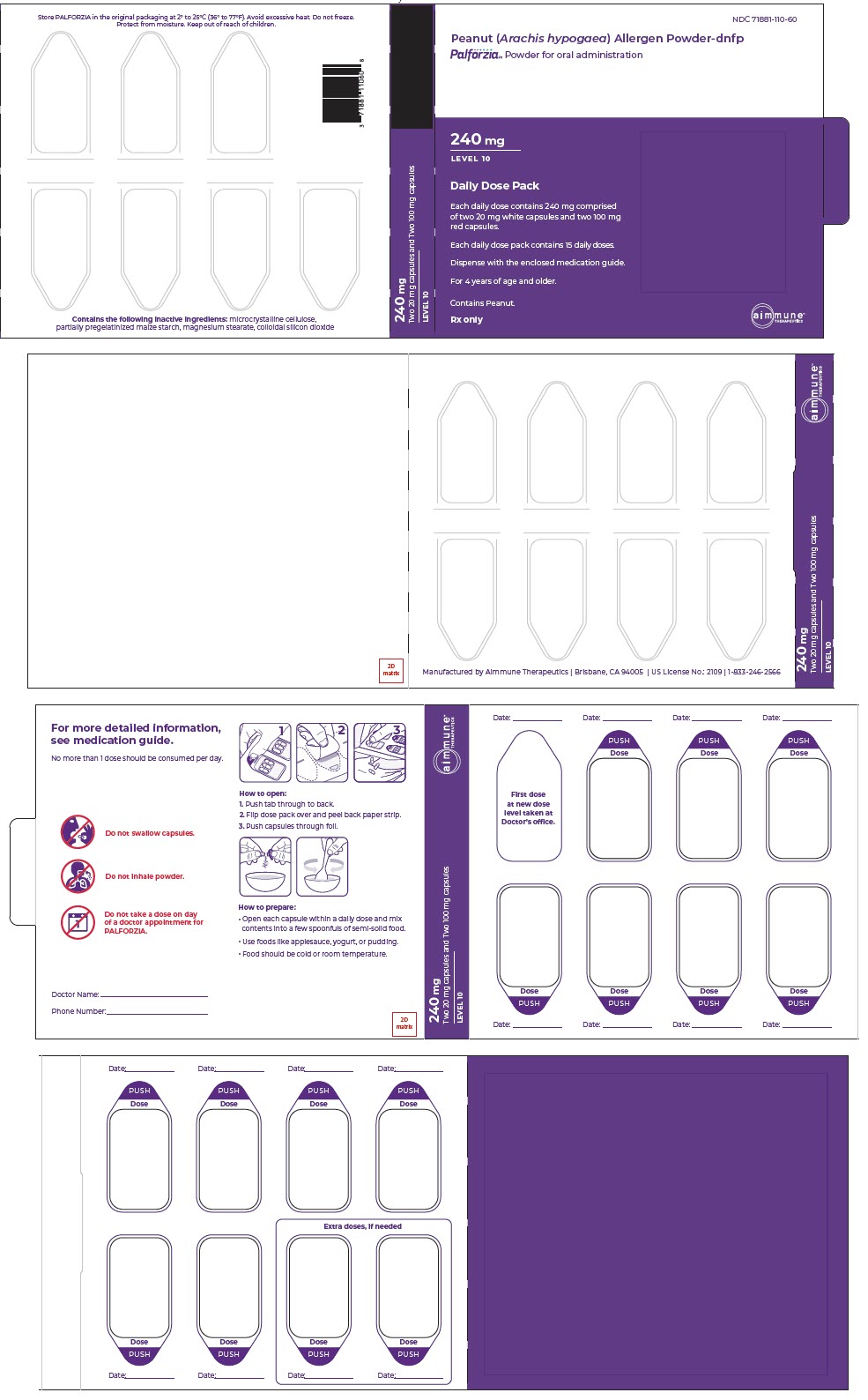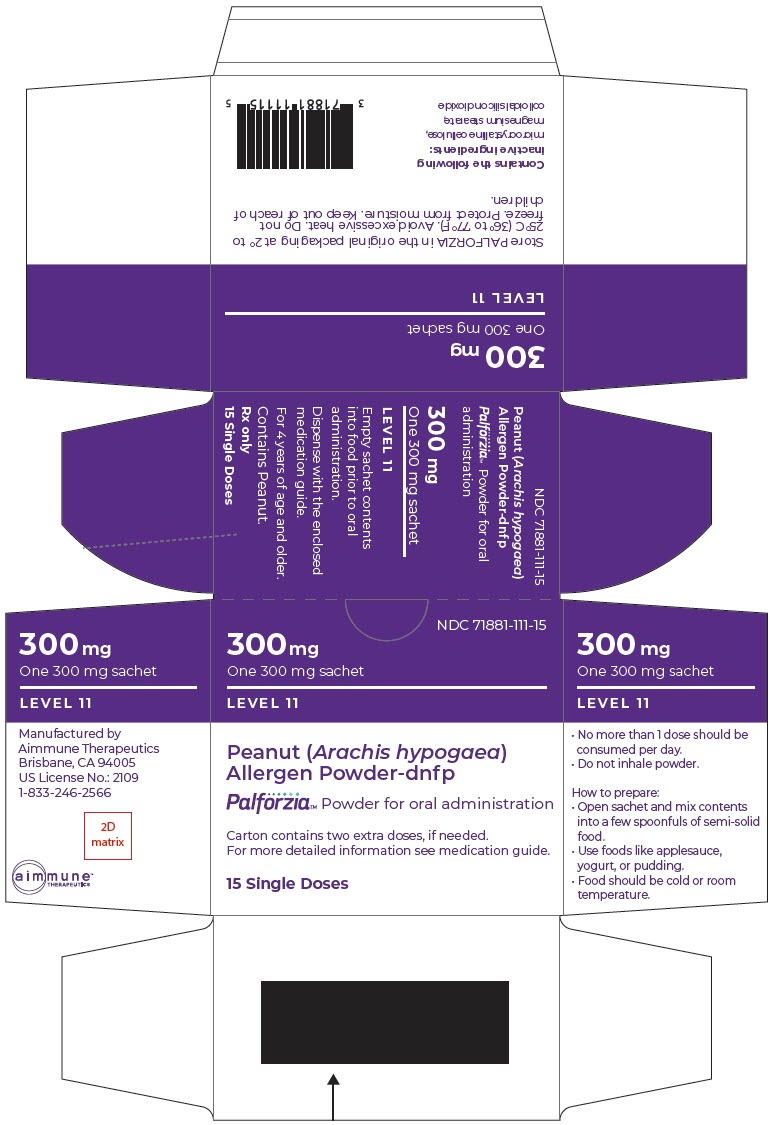 DRUG LABEL: PALFORZIA 

NDC: 71881-113 | Form: KIT | Route: ORAL
Manufacturer: Aimmune Therapeutics
Category: prescription | Type: HUMAN PRESCRIPTION DRUG LABEL
Date: 20230317

ACTIVE INGREDIENTS: PEANUT 0.5 mg/1 1; PEANUT 1 mg/1 1

HIGHLIGHTS OF PRESCRIBING INFORMATION

These highlights do not include all the information needed to use PALFORZIA safely and effectively. See Full Prescribing Information for PALFORZIA.
PALFORZIA [Peanut (Arachis hypogaea) Allergen Powder-dnfp] Powder for oral administration
Initial U.S. Approval: 2020

WARNING: ANAPHYLAXIS

See Full Prescribing Information for complete boxed warning.

- PALFORZIA can cause anaphylaxis, which may be life-threatening and can occur at any time during PALFORZIA therapy (5.1).
- Prescribe injectable epinephrine, instruct and train patients on its appropriate use, and instruct patients to seek immediate medical care upon its use (5.1).
- Do not administer PALFORZIA to patients with uncontrolled asthma (4).
- Dose modifications may be necessary following an anaphylactic reaction (2.5).
- Observe patients during and after administration of the Initial Dose Escalation and the first dose of each Up-Dosing level, for at least 60 minutes (2.4).
- PALFORZIA is available only through a restricted program called the PALFORZIA REMS (5.2).

1 INDICATIONS AND USAGE

PALFORZIA is an oral immunotherapy indicated for the mitigation of allergic reactions, including anaphylaxis, that may occur with accidental exposure to peanut. PALFORZIA is approved for use in patients with a confirmed diagnosis of peanut allergy. Initial Dose Escalation may be administered to patients aged 4 through 17 years. Up-Dosing and Maintenance may be continued in patients 4 years of age and older (2.4).

PALFORZIA is to be used in conjunction with a peanut-avoidant diet.

Limitation of Use: Not indicated for the emergency treatment of allergic reactions, including anaphylaxis.

2 DOSAGE AND ADMINISTRATION

For oral administration only (2)

- Do not swallow capsule(s).
- Do not inhale powder.
- Open capsule(s) or sachet and empty the entire dose of PALFORZIA powder onto refrigerated or room temperature semisolid food.
- Mix well.
- Consume the entire volume.

Initial Dose Escalation
Total Dose | Dose Configuration
0.5 mg | One 0.5 mg capsule
1 mg | One 1 mg capsule
1.5 mg | One 0.5 mg capsule; One 1 mg capsule
3 mg | Three 1 mg capsules
6 mg | Six 1 mg capsules

Up-Dosing
Total Daily Dose | Daily Dose Configuration
3 mg | Three 1 mg capsules
6 mg | Six 1 mg capsules
12 mg | Two 1 mg capsules; One 10 mg capsule
20 mg | One 20 mg capsule
40 mg | Two 20 mg capsules
80 mg | Four 20 mg capsules
120 mg | One 20 mg capsule; One 100 mg capsule
160 mg | Three 20 mg capsules; One 100 mg capsule
200 mg | Two 100 mg capsules
240 mg | Two 20 mg capsules; Two 100 mg capsules
300 mg | One 300 mg sachet

Maintenance
Total Daily Dose | Daily Dose Configuration
300 mg | One 300 mg sachet

3 DOSAGE FORMS AND STRENGTHS

Powder for oral administration supplied in 0.5 mg 1 mg, 10 mg, 20 mg and 100 mg Capsules or 300 mg Sachets.

4 CONTRAINDICATIONS

- Uncontrolled asthma (5.3).
- History of eosinophilic esophagitis or other eosinophilic gastrointestinal disease (5.4 and 5.5).

5 WARNINGS AND PRECAUTIONS

- Anaphylaxis: PALFORZIA can cause anaphylaxis. Educate patients to recognize the signs and symptoms of anaphylaxis. Prescribe injectable epinephrine, instruct and train patients on its appropriate use, and instruct patients to seek immediate medical care upon its use (5.1).
- Asthma: Ensure patients with asthma have their asthma under control prior to initiation of PALFORZIA. PALFORZIA should be temporarily withheld if the patient is experiencing an acute asthma exacerbation. PALFORZIA has not been studied in patients with severe asthma (5.3).
- Eosinophilic esophagitis: PALFORZIA is associated with eosinophilic esophagitis. Monitor patients for signs and symptoms and discontinue PALFORZIA if eosinophilic esophagitis is suspected (5.4).
- Gastrointestinal reactions: If patients develop chronic or recurrent local gastrointestinal allergic symptoms, consider dose modification or discontinuation of treatment (5.5).

6 ADVERSE REACTIONS

The most common adverse reactions reported in subjects treated with PALFORZIA (incidence ≥ 5% and at least 5 percentage points greater than that reported in subjects treated with placebo) are abdominal pain, vomiting, nausea, oral pruritus, oral paresthesia, throat irritation, cough, rhinorrhea, sneezing, throat tightness, wheezing, dyspnea, pruritus, urticaria, anaphylactic reaction, and ear pruritus (6.1).

To report SUSPECTED ADVERSE REACTIONS, contact Aimmune Therapeutics at toll-free phone 1-833-246-2566 or FDA at 1-800-FDA-1088 or www.fda.gov/medwatch.

FULL PRESCRIBING INFORMATION

WARNING: ANAPHYLAXIS

- PALFORZIA can cause anaphylaxis, which may be life-threatening and can occur at any time during PALFORZIA therapy [see Warnings and Precautions (5.1)] .
- Prescribe injectable epinephrine, instruct and train patients on its appropriate use, and instruct patients to seek immediate medical care upon its use [see Warnings and Precautions (5.1)] .
- Do not administer PALFORZIA to patients with uncontrolled asthma [see Contraindications (4)] .
- Dose modifications may be necessary following an anaphylactic reaction [see Dosage and Administration (2.5)] .
- Observe patients during and after administration of the Initial Dose Escalation and the first dose of each Up-Dosing level, for at least 60 minutes [see Dosage and Administration (2.4)] .
- Because of the risk of anaphylaxis, PALFORZIA is available only through a restricted program under a Risk Evaluation and Mitigation Strategy (REMS) called the PALFORZIA REMS [see Warnings and Precautions (5.2)] .

1 INDICATIONS AND USAGE

PALFORZIA is an oral immunotherapy indicated for the mitigation of allergic reactions, including anaphylaxis, that may occur with accidental exposure to peanut. PALFORZIA is approved for use in patients with a confirmed diagnosis of peanut allergy. Initial Dose Escalation may be administered to patients aged 4 through 17 years. Up-Dosing and Maintenance may be continued in patients 4 years of age and older [see Dosage and Administration (2.4)] .

PALFORZIA is to be used in conjunction with a peanut-avoidant diet.

Limitation of Use: Not indicated for the emergency treatment of allergic reactions, including anaphylaxis.

2 DOSAGE AND ADMINISTRATION

2.1 Important Considerations Prior to Initiation and During Therapy

Verify that the patient has injectable epinephrine and instruct patient on its appropriate use [see Warnings and Precautions (5.2)] .

2.2 Dosage

Treatment with PALFORZIA is administered in 3 sequential phases: Initial Dose Escalation, Up-Dosing, and Maintenance.

The dose configurations for each phase of dosing are provided in Table 1 through Table 3.

Table 1: Dosing Configuration for Initial Dose Escalation (Single Day Dose Escalation)
Dose Level | Total Dose | Dose Configuration
A | 0.5 mg | One 0.5 mg capsule
B | 1 mg | One 1 mg capsule
C | 1.5 mg | One 0.5 mg capsule; One 1 mg capsule
D | 3 mg | Three 1 mg capsules
E | 6 mg | Six 1 mg capsules
Initial Dose Escalation supplied as a single card consisting of 5 blisters containing a total of 13 capsules.

Table 2: Daily Dosing Configuration for Up-Dosing
Dose Level | Total Daily Dose | Daily Dose Configuration | Dose Duration (weeks)
1 | 3 mg | Three 1 mg capsules | 2
2 | 6 mg | Six 1 mg capsules | 2
3 | 12 mg | Two 1 mg capsules; One 10 mg capsule | 2
4 | 20 mg | One 20 mg capsule | 2
5 | 40 mg | Two 20 mg capsules | 2
6 | 80 mg | Four 20 mg capsules | 2
7 | 120 mg | One 20 mg capsule; One 100 mg capsule | 2
8 | 160 mg | Three 20 mg capsules; One 100 mg capsule | 2
9 | 200 mg | Two 100 mg capsules | 2
10 | 240 mg | Two 20 mg capsules; Two 100 mg capsules | 2
11 | 300 mg | One 300 mg sachet | 2

Table 3: Daily Dosing Configuration for Maintenance
Dose Level | Total Daily Dose | Daily Dose Configuration
11 | 300 mg | One 300 mg sachet

2.3 Preparation and Handling

PALFORZIA is to be administered orally.

- Open capsule(s) or sachet and empty the entire dose of PALFORZIA powder onto a few spoonfuls of refrigerated or room temperature semisolid food (e.g., applesauce, yogurt, pudding). Do not use liquid (e.g., milk, water, juice) to prepare.
- Mix well.
- Consume the entire volume of the prepared mixture promptly.
- Dispose of the opened capsule(s) or sachet.
- Wash hands immediately after handling PALFORZIA capsule(s) or sachets.
- Dispose of all unused PALFORZIA.

2.4 Administration

- For oral administration only.
- Do not swallow capsule(s).
- Do not inhale powder.

Initial Dose Escalation

Initial Dose Escalation is administered on a single day under the supervision of a health care professional in a health care setting with the ability to manage potentially severe allergic reactions, including anaphylaxis.

Initial Dose Escalation is administered in sequential order on a single day beginning at Level A (5 Levels A-E, 0.5-6 mg; Table 1).

Each dose should be separated by an observation period of 20 to 30 minutes.

No dose level should be omitted.

Observe patients after the last dose for at least 60 minutes until suitable for discharge.

Discontinue PALFORZIA if symptoms requiring medical intervention (e.g., use of epinephrine) occur with any dose during Initial Dose Escalation [see Dosage and Administration (2.5)] .

Patients who tolerate at least the 3 mg single dose (Level D) of PALFORZIA during Initial Dose Escalation must return to the health care setting for initiation of Up-Dosing.

If possible, begin Up-Dosing the day after Initial Dose Escalation.

Repeat Initial Dose Escalation in a health care setting if the patient is unable to begin Up-Dosing within 4 days.

Up-Dosing

Complete Initial Dose Escalation before starting Up-Dosing.

Up-Dosing consists of 11 dose levels and is initiated at a 3 mg dose (Level 1).

The first dose of each new Up-Dosing level is administered under the supervision of a health care professional in a health care setting with the ability to manage potentially severe allergic reactions, including anaphylaxis.

Observe patients after administering the first dose of a new Up-Dosing level for at least 60 minutes until suitable for discharge.

If the patient tolerates the first dose of the increased dose level, the patient may continue that dose level at home. Each dose should be consumed daily with a meal at approximately the same time each day, preferably in the evening.

Administer all the dose levels in Table 2 in sequential order at 2-week intervals if tolerated.

No dose level should be omitted.

Do not progress through Up-Dosing more rapidly than shown in Table 2.

No more than 1 dose should be consumed per day. Instruct patients not to consume a dose at home on the same day as a dose consumed in the clinic.

Consider dose modification or discontinuation for patients who do not tolerate Up-Dosing as described in Table 2 [see Dosage and Administration (2.5)] .

Maintenance

Complete all dose levels of Up-Dosing before starting Maintenance.

The Maintenance dose of PALFORZIA is 300 mg daily.

Daily Maintenance is required to maintain the effect of PALFORZIA.

During Maintenance, contact patient at regular intervals to assess for adverse reactions to PALFORZIA.

2.5 Schedule Modification and Product Discontinuation

Dose Modification

Dose modifications are not appropriate during Initial Dose Escalation.

Temporary dose modification of PALFORZIA may be required for patients who experience allergic reactions during Up-Dosing or Maintenance, for patients who miss doses, or for practical reasons of patient management. Allergic reactions, including gastrointestinal reactions, that are severe, recurrent, bothersome, or last longer than 90 minutes during Up-Dosing or Maintenance should be actively managed with dose modifications. Use clinical judgment to determine the best course of action, which can include maintaining the dose level for longer than 2 weeks, reducing, withholding, or discontinuing PALFORZIA doses.

Management of Consecutive Missed Doses

Following 1 to 2 consecutive days of missed doses, patients may resume PALFORZIA at the same dose level. Data are insufficient to inform resumption of PALFORZIA following 3 or more consecutive days of missed doses. Patients who miss 3 or more consecutive days of PALFORZIA should consult their healthcare providers; resumption of PALFORZIA should be done under medical supervision.

Discontinuation of PALFORZIA

Discontinue treatment with PALFORZIA for:

- Patients who are unable to tolerate doses up to and including the 3 mg dose during Initial Dose Escalation
- Patients with suspected eosinophilic esophagitis [see Warnings and Precautions (5.4 and 5.5)]
- Patients unable to comply with the daily dosing requirements
- Patients with recurrent asthma exacerbations or persistent loss of asthma control

3 DOSAGE FORMS AND STRENGTHS

PALFORZIA powder description and dosage strengths are as follows:

- 0.5 mg: white to off-white fine granular oral powder (may contain clumps) in white opaque capsules with Aimmune printed on the body and 0.5 mg printed on the cap in grey ink
- 1 mg: white to off-white fine granular oral powder (may contain clumps) in red opaque capsules with Aimmune printed on the body and 1 mg printed on the cap in white ink
- 10 mg: white to off-white fine granular oral powder (may contain clumps) in blue opaque capsules with Aimmune printed on the body and 10 mg printed on the cap in white ink
- 20 mg: off-white to light beige fine granular oral powder (may contain clumps) in white opaque capsules with Aimmune printed on the body and 20 mg printed on the cap in grey ink
- 100 mg: beige fine oral powder (may contain clumps) in red opaque capsules with Aimmune printed on the body and 100 mg printed on the cap in white ink
- 300 mg: beige fine oral powder (may contain clumps) in white foil-laminate sachets with printed information

Combinations of capsules for doses are described in Dosage and Administration (2.2).

4 CONTRAINDICATIONS

PALFORZIA is contraindicated in patients with the following:

- Uncontrolled asthma [see Warnings and Precautions (5.3)]
- A history of eosinophilic esophagitis and other eosinophilic gastrointestinal disease [see Warnings and Precautions (5.4 and 5.5)]

5 WARNINGS AND PRECAUTIONS

5.1 Anaphylaxis

PALFORZIA can cause anaphylaxis, which may be life-threatening.

Anaphylaxis has been reported during all phases of PALFORZIA dosing, including Maintenance and in subjects who have undergone recommended Up-Dosing and dose modification procedures.

In 709 PALFORZIA-treated subjects and 292 placebo-treated subjects in the placebo-controlled population in Studies 1 and 2 combined [see Adverse Reactions (6.1)] , anaphylaxis was reported in 9.4% of PALFORZIA-treated subjects compared with 3.8% of placebo-treated subjects during Initial Dose Escalation and Up-Dosing combined, and in 8.7% of PALFORZIA-treated subjects compared with 1.7% of placebo-treated subjects during Maintenance in Study 1. Epinephrine use for any reason was reported in 10.4% of PALFORZIA-treated subjects compared with 4.8% of placebo-treated subjects during Initial Dose Escalation and Up-Dosing combined, and in 7.7% of PALFORZIA-treated subjects compared with 3.4% of placebo-treated subjects during Maintenance dosing in Study 1. Time to onset of anaphylaxis occurred within 2 hours after dosing in 70% of reactions, greater than 2 hours and up to 10 hours in 18% of reactions, and greater than 10 hours in 12% of reactions among PALFORZIA-treated subjects.

Do not initiate PALFORZIA treatment in a patient who has had severe or life-threatening anaphylaxis within the previous 60 days. PALFORZIA may not be suitable for patients with certain medical conditions that may reduce the ability to survive anaphylaxis, including but not limited to markedly compromised lung function, severe mast cell disorder, or cardiovascular disease. In addition, PALFORZIA may not be suitable for patients taking medications that can inhibit or potentiate the effects of epinephrine.

All Initial Dose Escalation doses and the first dose of each Up-Dosing level must be administered under observation in a health care setting [see Dosage and Administration (2.5)] . Prior to initiating PALFORZIA treatment, educate patients to recognize the signs and symptoms of anaphylaxis. Prescribe injectable epinephrine, instruct and train patients on its appropriate use, and instruct patients to seek immediate medical care upon its use. Instruct patients to contact their health care professional before administering the next dose of PALFORZIA if anaphylaxis or symptoms of an escalating or persistent allergic reaction occur as dose modification may be necessary [see Dosage and Administration (2.4)] .

Patients may be more likely to experience allergic reactions following PALFORZIA administration in the presence of cofactors such as exercise, hot water exposure, intercurrent illness (e.g., viral infection), or fasting. Other potential cofactors may include menstruation, sleep deprivation, nonsteroidal anti-inflammatory drug use, or uncontrolled asthma. Patients should be proactively counseled about the potential for the increased risk of anaphylaxis in the presence of these cofactors. If possible, adjust the time of dosing to avoid these cofactors. If it is not possible to avoid these cofactors, consider withholding PALFORZIA temporarily.

If appropriate to re-start administering PALFORZIA in patients who experienced anaphylaxis while on PALFORZIA or who had doses withheld to avoid increased risk of anaphylaxis, consider a dose reduction and dose re-escalation based on clinical judgment [see Dosage and Administration (2.5)] .

PALFORZIA is available only through a restricted program under a REMS [see Warnings and Precautions (5.2)] .

5.2 PALFORZIA REMS Program

PALFORZIA is available only through a restricted program under a Risk Evaluation and Mitigation Strategy (REMS) called the PALFORZIA REMS because of the risk of anaphylaxis [see Warnings and Precautions (5.1)] .

Notable requirements of the PALFORZIA REMS include the following:

- Health care providers who prescribe PALFORZIA must be certified with the program by enrolling.
- Health care settings must be certified in the program, have on-site access to equipment and personnel trained to manage anaphylaxis, and establish policies and procedures to verify that patients are monitored during and after the Initial Dose Escalation and first dose of each Up-Dosing level.
- Patients must be enrolled in the program prior to initiation of PALFORZIA treatment and must be informed of the need to have injectable epinephrine available for immediate use at all times, the need for monitoring with the Initial Dose Escalation and first dose of each Up-Dosing level, the need for continued dietary peanut avoidance, and how to recognize the signs and symptoms of anaphylaxis.
- Pharmacies must be certified with the program and must only dispense PALFORZIA to health care settings that are certified or to patients who are enrolled depending on the treatment phase.

Further information, including a list of certified prescribers, health care settings, and pharmacies, is available at www.PALFORZIAREMS.com or 1-844-PALFORZ (1-844-725-3679).

5.3 Asthma

Uncontrolled asthma is a risk factor for a serious outcome, including death, in anaphylaxis. Ensure patients with asthma have their asthma under control prior to initiation of PALFORZIA.

PALFORZIA should be temporarily withheld if the patient is experiencing an acute asthma exacerbation. Following resolution of the exacerbation, resumption of PALFORZIA should be undertaken cautiously [see Dosage and Administration (2.5)] . Re-evaluate patients who have recurrent asthma exacerbations and consider discontinuation of PALFORZIA. PALFORZIA has not been studied in subjects with severe asthma, persistently uncontrolled asthma, or patients on long-term systemic corticosteroid therapy.

5.4 Eosinophilic Gastrointestinal Disease

In clinical studies, 28 of 1050 (2.7%) subjects were referred for a gastroenterology evaluation and 17 of these 28 subjects reported undergoing an esophagogastroduodenoscopy (EGD). Of subjects who underwent an EGD, 12 were diagnosed with biopsy-confirmed eosinophilic esophagitis while receiving PALFORZIA compared with 0 of 292 (0%) subjects receiving placebo. After discontinuation of PALFORZIA, symptomatic improvement was reported in 12 of 12 subjects. In 8 subjects with available follow-up biopsy results, eosinophilic esophagitis was resolved in 6 subjects and improved in 2 subjects [see Contraindications (4)] .

Discontinue PALFORZIA and consider a diagnosis of eosinophilic esophagitis in patients who experience severe or persistent gastrointestinal symptoms, including dysphagia, vomiting, nausea, gastroesophageal reflux, chest pain, or abdominal pain [see Warnings and Precautions (5.5)] .

5.5 Gastrointestinal Adverse Reactions

Gastrointestinal adverse reactions, including abdominal pain, vomiting, nausea, oral pruritus, and oral paresthesia, were commonly reported in PALFORZIA-treated subjects in the placebo-controlled clinical study population [see Adverse Reactions (6, Table 4)] . Dose modification should be considered for patients who report these reactions [see Dosage and Administration (2.5)]. For severe or persistent gastrointestinal symptoms consider a diagnosis of eosinophilic esophagitis [see Warnings and Precautions (5.4)] .

6 ADVERSE REACTIONS

6.1 Clinical Trial Experience

Use of PALFORZIA has been associated with:

- Anaphylaxis [see Warnings and Precautions (5.1)]
- Eosinophilic esophagitis [see Warnings and Precautions (5.4)]

Because clinical trials are conducted under widely varying conditions, adverse reaction rates observed in clinical trials of a drug cannot be directly compared with the adverse reaction rates in clinical trials of another drug and may not reflect the rates observed in practice.

The clinical data for PALFORZIA reflect exposure in 709 peanut-allergic subjects enrolled in two phase 3, double-blind, placebo-controlled trials (Study 1 and Study 2), and in long-term, open-label, follow-on studies. In Study 1, subjects were Up-Dosed for 20-40 weeks followed by Maintenance dosing for 24-28 weeks. In Study 2 subjects were Up-Dosed for 20-40 weeks up to a 300 mg daily dose with no extended Maintenance dosing. In these studies, subjects recorded adverse reactions daily in an electronic diary card throughout the study duration.

Study 1 (NCT02635776) was a randomized, double-blind, placebo-controlled efficacy and safety study conducted in the United States, Canada, and Europe evaluating PALFORZIA versus placebo in 555 subjects aged 4 through 55 years with peanut allergy. Subjects were required to have serum IgE to peanut ≥ 0.35 kUA/L within 12 months before study entry and/or a mean wheal diameter on skin prick test to peanut ≥ 3 mm greater than the negative control. The primary analysis population was aged 4 through 17 years, 78% white and 57% male. At study entry, subjects reacted at 100 mg or less of peanut protein in a double-blind, placebo-controlled food challenge (DBPCFC). The primary analysis was conducted in 496 subjects aged 4 through 17 years (PALFORZIA, N = 372; placebo, N = 124). Of the subjects aged 4 through 17 years treated with PALFORZIA, 72% had a medical history of anaphylactic reactions to peanut, 66% reported multiple food allergies, 63% had a medical history of atopic dermatitis, and 53% had a present or previous diagnosis of asthma. Subjects with severe persistent or uncontrolled asthma were excluded.

Study 2 (NCT03126227) was a randomized, double-blind, placebo-controlled safety study conducted in the United States and Canada evaluating PALFORZIA versus placebo in 506 subjects aged 4 through 17 years with peanut allergy. Subjects were required to have a clinical history of peanut allergy including onset of characteristic allergic signs and symptoms within 2 hours of known oral exposure to peanut, serum IgE to peanut of ≥ 14 kUA/L and a mean wheal diameter on skin prick test ≥ 8 mm greater than the negative control at screening. Subjects were not required to complete a DBPCFC for study entry. The study duration was approximately 6 months and compared the safety and tolerability of PALFORZIA (N = 337) with placebo (N = 168). Most subjects were male (63%) and white (79%). Of the subjects treated with PALFORZIA, 60.5% had a medical history of anaphylactic reactions, 65.0% reported multiple food allergies, 57.9% had a medical history of atopic dermatitis, and 52.2% had a present or previous diagnosis of asthma. Subjects with severe persistent or uncontrolled asthma were excluded.

Across these two phase 3, double-blind, placebo-controlled, randomized clinical studies the most common adverse reactions in subjects treated with PALFORZIA (incidence ≥ 5% and at least 5 percentage points greater than in subjects treated with placebo) were gastrointestinal, respiratory, and skin symptoms commonly associated with allergic reactions, as shown in Table 4.

Table 4: Treatment-Emergent Adverse Reactions in ≥ 5% of PALFORZIA-Treated Subjects and ≥ 5% Percentage Points Greater Than Placebo-Treated Subjects in any Dosing Phase (Aged 4 through 17 Years)
System Organ Class / Preferred Term [Adverse events were coded to system organ class and preferred term using the MedDRA, version 19.1.] | Study 1 & Study 2 IDE PALFORZIA (N = 709) | Study 1 & Study 2 IDE Placebo (N = 292) | Study 1 & Study 2 Up-Dosing PALFORZIA (N = 693) | Study 1 & Study 2 Up-Dosing Placebo (N = 289) | Study 1 [In Study 2, no adverse reactions ≥ 5% were reported in subjects following treatment with 300 mg PALFORZIA (N = 265).] 300 mg PALFORZIA (N = 310) | Study 1 300 mg Placebo (N = 118)
Gastrointestinal disorders
Abdominal pain [Includes preferred terms of abdominal pain, abdominal pain upper, and abdominal discomfort.] | 185 (26.1%) | 24 (8.2%) | 465 (67.1%) | 100 (34.6%) | 90 (29.0%) | 20 (16.9%)
Vomiting | 22 (3.1%) | 2 (0.7%) | 253 (36.5%) | 47 (16.3%) | 50 (16.1%) | 14 (11.9%)
Nausea | 60 (8.5%) | 2 (0.7%) | 224 (32.3%) | 41 (14.2%) | 45 (14.5%) | 8 (6.8%)
Oral pruritus [Includes preferred terms of oral pruritus, tongue pruritis, and lip pruritus.] | 62 (8.7%) | 9 (3.1%) | 216 (31.2%) | 30 (10.4%) | 51 (16.5%) | 7 (5.9%)
Oral paresthesia | 13 (1.8%) | 7 (2.4%) | 94 (13.6%) | 11 (3.8%) | 23 (7.4%) | 2 (1.7%)
Respiratory, thoracic, and mediastinal disorders
Throat irritation | 66 (9.3%) | 15 (5.1%) | 279 (40.3%) | 49 (17.0%) | 43 (13.9%) | 11 (9.3%)
Cough | 18 (2.5%) | 1 (0.3%) | 221 (31.9%) | 68 (23.5%) | 61 (19.7%) | 22 (18.6%)
Rhinorrhea | 9 (1.3%) | 4 (1.4%) | 145 (20.9%) | 50 (17.3%) | 46 (14.8%) | 9 (7.6%)
Sneezing | 24 (3.4%) | 8 (2.7%) | 140 (20.2%) | 31 (10.7%) | 33 (10.6%) | 5 (4.2%)
Throat tightness | 18 (2.5%) | 3 (1.0%) | 98 (14.1%) | 8 (2.8%) | 20 (6.5%) | 0 (0.0%)
Wheezing | 4 (0.6%) | 0 (0.0%) | 85 (12.3%) | 21 (7.3%) | 19 (6.1%) | 10 (8.5%)
Dyspnea | 2 (0.3%) | 1 (0.3%) | 53 (7.6%) | 5 (1.7%) | 17 (5.5%) | 1 (0.8%)
Skin and subcutaneous tissue disorders
Pruritus | 56 (7.9%) | 16 (5.5%) | 225 (32.5%) | 59 (20.4%) | 45 (14.5%) | 14 (11.9%)
Urticaria | 28 (3.9%) | 10 (3.4%) | 197 (28.4%) | 54 (18.7%) | 63 (20.3%) | 17 (14.4%)
Immune system disorders
Anaphylactic reaction [The anaphylactic reaction preferred term includes systemic allergic reactions of any severity, of which severe anaphylaxis was reported in 4 PALFORZIA-treated subjects (0.6%) during Up-Dosing and 1 PALFORZIA-treated subject (0.3%) during Maintenance.] | 5 (0.7%) | 1 (0.3%) | 63 (9.1%) | 10 (3.5%) | 27 (8.7%) | 2 (1.7%)
Ear and labyrinth disorders
Ear pruritus | 5 (0.7%) | 1 (0.3%) | 41 (5.9%) | 2 (0.7%) | 7 (2.3%) | 0 (0.0%)
At each level of summarization (any event, system organ class, or preferred term) subjects with more than 1 adverse reaction were counted only once within each study period.
IDE, Initial Dose Escalation; MedDRA, Medical Dictionary for Regulatory Activities.

A total of 155 (21.9%) PALFORZIA-treated subjects and 19 (6.5%) placebo-treated subjects discontinued for any reason in Studies 1 and 2. Adverse reactions led to study discontinuation in 9.2% PALFORZIA-treated subjects and 1.7% placebo-treated subjects during Initial Dose Escalation and Up-Dosing combined in Studies 1 and 2, and 1.0% PALFORZIA-treated subjects and no placebo-treated subjects during Maintenance dosing in Study 1. Gastrointestinal reactions were the most common reason leading to discontinuation of study product during Initial Dose Escalation and Up-Dosing combined (6.5% PALFORZIA, 1.0% placebo), followed by respiratory disorders (2.3% PALFORZIA, 1.0% placebo) in Studies 1 and 2.

The timing of symptoms relative to exposure to PALFORZIA was evaluated for dosing that occurred within a clinical setting during Initial Dose Escalation and on the day of initiation of each new dose level during the Up-Dosing phase (every 2 weeks) and during monthly Maintenance visits. Symptoms occurring in the clinic following any dose of PALFORZIA had a median time to onset of 4 minutes for 502 subjects (70.8%). The median time to resolution of the last symptom was 37 minutes.

8 USE IN SPECIFIC POPULATIONS

8.1 Pregnancy

Pregnancy Registry

There is a pregnancy exposure registry that monitors pregnancy outcomes in women exposed to PALFORZIA during pregnancy. Women exposed to PALFORZIA during pregnancy or their health care professionals are encouraged to contact Aimmune by calling 1-833-246-2566.

Risk Summary

All pregnancies have a risk of birth defect, loss, or other adverse outcomes. In the U.S. general population, the estimated background risk of major birth defects and miscarriage in clinically recognized pregnancies is 2% to 4% and 15% to 20%, respectively. No human or animal data are available to establish the presence or absence of the risks due to PALFORZIA in pregnant women.

Clinical Considerations

Disease-associated maternal and/or embryo/fetal risk

Anaphylaxis may occur following accidental exposure to peanut in peanut-allergic pregnant women. Anaphylaxis can cause a dangerous decrease in blood pressure, which could result in compromised placental perfusion and significant risk to a fetus.

Maternal adverse reactions

PALFORZIA may cause anaphylaxis [see Warnings and Precautions (5.1) and Fetal/Neonatal adverse reactions] .

Fetal/Neonatal adverse reactions

PALFORZIA may cause anaphylaxis [see Warnings and Precautions (5.1)] . Anaphylaxis can cause a dangerous decrease in blood pressure, which could result in compromised placental perfusion and significant risk to a fetus.

8.2 Lactation

Risk Summary

There are no data available on the presence of PALFORZIA in human milk, the effects on the breastfed infant, or the effects on milk production. The developmental and health benefits of breastfeeding should be considered, along with the mother's clinical need for PALFORZIA and any other potential adverse effects on the breastfed child from PALFORZIA or from the underlying maternal condition.

8.4 Pediatric Use

Safety and effectiveness of PALFORZIA have not been established in persons younger than 4 years of age.

10 OVERDOSAGE

Symptoms of overdose in patients with peanut allergy may include hypersensitivity reactions such as anaphylaxis or local gastrointestinal allergic reactions [see Warnings and Precautions (5.1 and 5.5)] . In case of severe symptoms such as difficulty in swallowing, difficulty in breathing, changes in voice, feeling of fullness in the throat, or anaphylaxis, patients should be instructed to use epinephrine and seek immediate medical assistance [see Warnings and Precautions (5.1) and Patient Counseling Information (17)] .

11 DESCRIPTION

PALFORZIA (Peanut (Arachis hypogaea) Allergen Powder-dnfp) is a powder for oral administration. PALFORZIA is manufactured from defatted peanut flour. PALFORZIA is available in capsules containing 0.5 mg, 1 mg, 10 mg, 20 mg, and 100 mg peanut protein, and a sachet containing 300 mg peanut protein. Each dose meets specifications for quantities of Ara h 1, Ara h 2, and Ara h 6, measured by immunoassay alone or in combination with high performance liquid chromatography.

Depending on the dose level, PALFORZIA contains the following inactive ingredients: microcrystalline cellulose, partially pregelatinized maize starch (0.5 mg, 1 mg, 10 mg, 20 mg capsule presentations only), magnesium stearate, and colloidal silicon dioxide.

12 CLINICAL PHARMACOLOGY

12.1 Mechanism of Action

The mechanism of action of PALFORZIA has not been established.

13 NONCLINICAL TOXICOLOGY

13.1 Carcinogenesis, Mutagenesis, Impairment of Fertility

PALFORZIA has not been evaluated for carcinogenicity, genotoxicity, mutagenic potential, or impairment of male or female fertility in animals.

14 CLINICAL STUDIES

The efficacy of PALFORZIA for the mitigation of allergic reactions, including anaphylaxis, in patients with peanut allergy was investigated in Study 1 (NCT02635776). Study 1 was a phase 3, randomized, double-blind, placebo-controlled study of the efficacy and safety of PALFORZIA in patients with peanut allergy aged 4 through 55 years in the United States, Canada, and Europe. The primary analysis population consisted of 496 subjects (PALFORZIA, N = 372; placebo, N = 124) aged 4 through 17 years in the intent-to-treat (ITT) population who received at least 1 dose of study treatment. After an Initial Dose Escalation ranging from 0.5 mg to 6 mg on Day 1 and confirmation of tolerability of the 3 mg dose on Day 2, subjects underwent Up-Dosing for 20-40 weeks starting at 3 mg until the 300 mg dose was reached. The Up-Dosing period varied for each subject depending on how the dose was tolerated. Subjects then underwent 24-28 weeks of Maintenance immunotherapy with 300 mg PALFORZIA until the end of the study. At the end of the Maintenance period, subjects completed an exit DBPCFC to approximate an accidental exposure to peanut and to assess their ability to tolerate increasing amounts of peanut protein with no more than mild allergic symptoms.

The primary efficacy endpoint was the percentage of subjects tolerating a single dose of 600 mg peanut protein in the exit DBPCFC with no more than mild allergic symptoms after 6 months of Maintenance treatment. The primary efficacy endpoint was considered met if the lower bound of the 95% confidence interval (CI) for the difference in response rates between the treatment and the placebo groups was greater than the prespecified margin of 15%. Key secondary endpoints included the comparisons of the response rates after single doses of 300 mg and 1000 mg peanut protein as well as a comparison of the maximum severity of symptoms at any challenge dose of peanut protein during the exit DBPCFC. The key secondary endpoints were to be evaluated for statistical significance (two-sided p < 0.05) only if the primary endpoint and all the preceding tests in the hierarchy were statistically significant in favor of PALFORZIA. Response rates at the exit DBPCFC for the ITT population are shown in Table 5. The maximum severity of symptoms at any challenge is shown in Table 6.

Table 5: Response Rates at the Exit DBPCFC in Study 1 (ITT Population, 4 through 17 Years)
Peanut challenge dose, single dose | 300 mg [Secondary endpoint was considered met if the Farrington-Manning test for a non-zero treatment difference was significant at the two-sided 0.05 level.] | 600 mg [The primary efficacy endpoint was considered met if the lower bound of the Farrington-Manning 95% CI was greater than the prespecified margin of 15 percentage points.] | 1000 mg
PALFORZIA (N = 372) | 76.6% | 67.2% | 50.3%
Placebo (N = 124) | 8.1% | 4.0% | 2.4%
Treatment difference (95% CI) | 68.5% (58.6%, 78.5%) | 63.2% (53.0%, 73.3%) | 47.8% (38.0%, 57.7%)
P-value | < 0.0001 | < 0.0001 | < 0.0001
Subjects without an exit DBPCFC were counted as non-responders.
CI, confidence interval, DBPCFC, double-blind, placebo-controlled food challenge; ITT, intent-to-treat.

The completer population consisted of all subjects aged 4 through 17 years in the ITT population who stayed on treatment and had an evaluable exit DBPCFC (296 PALFORZIA, 116 placebo). In the completer population, the proportion of subjects who tolerated single highest doses of 300 mg, 600 mg, and 1000 mg with no more than mild symptoms at the exit DBPCFC were 96.3%, 84.5%, and 63.2%, respectively for PALFORZIA-treated subjects compared with 8.6%, 4.3%, and 2.6% for placebo-treated subjects.

Table 6: Maximum Severity of Symptoms at Any Challenge Dose During the Exit DBPCFC (ITT Population, 4 through 17 Years)
Symptom Severity | PALFORZIA N = 372 | Placebo N = 124
None | 37.6% | 2.4%
Mild | 32.0% | 28.2%
Moderate | 25.3% | 58.9%
Severe [Includes severe symptoms and life-threatening or fatal reactions. No subjects had symptoms considered life-threatening or fatal.] | 5.1% | 10.5%
Subjects without an exit DBPCFC were assigned the maximum severity during the screening DBPCFC, which equates to no change from screening.
P-value < 0.0001; symptom severity was assigned with equally spaced scores (e.g. 0, 1, 2, and 3 for none, mild, moderate, and severe, respectively), and the difference of mean scores between the two treatment arms was tested using the Cochran-Mantel-Haenszel statistic stratified by geographic region (North America, Europe).
DBPCFC, double-blind, placebo-controlled food challenge; ITT, intent-to-treat.

There are no data available on the efficacy of PALFORZIA in individuals who did not progress onto Maintenance therapy.

16 HOW SUPPLIED/STORAGE AND HANDLING

Table 7: PALFORZIA Commercial Packaging Presentations
Packaging Presentation | Kit Components (Capsules or Sachets) | Number of Doses per Kit | NDC Numbers (Kit Components) | NDC Number (Kit)
Initial Dose | Each pack contains 13 capsules: | 5 |  | 71881-113-13
Escalation | • 0.5 mg (Level A)
 | One 0.5 mg capsule |  | 71881-121-01
 | • 1 mg (Level B)
 | One 1 mg capsule |  | 71881-122-01
 | • 1.5 mg (Level C)
 | One 0.5 mg capsule; |  | 71881-121-01
 | One 1 mg capsule |  | 71881-122-01
 | • 3 mg (Level D)
 | Three 1 mg capsules |  | 71881-122-01
 | • 6 mg (Level E)
 | Six 1 mg capsules |  | 71881-122-01
Up-Dosing
3 mg | Forty-five 1 mg capsules | 15 | 71881-122-01 | 71881-101-45
(Level 1)
6 mg | Ninety 1 mg capsules | 15 | 71881-122-01 | 71881-102-90
(Level 2)
12 mg | Thirty 1 mg capsules; | 15 | 71881-122-01 | 71881-103-45
(Level 3) | Fifteen 10 mg capsules |  | 71881-123-01
20 mg | Fifteen 20 mg capsules | 15 | 71881-124-01 | 71881-104-15
(Level 4)
40 mg | Thirty 20 mg capsules | 15 | 71881-124-01 | 71881-105-30
(Level 5)
80 mg | Sixty 20 mg capsules | 15 | 71881-124-01 | 71881-106-60
(Level 6)
120 mg | Fifteen 20 mg capsules; | 15 | 71881-124-01 | 71881-107-30
(Level 7) | Fifteen 100 mg capsules |  | 71881-125-01
160 mg | Forty-five 20 mg capsules; | 15 | 71881-124-01 | 71881-108-60
(Level 8) | Fifteen 100 mg capsules |  | 71881-125-01
200 mg | Thirty 100 mg capsules | 15 | 71881-125-01 | 71881-109-30
(Level 9)
240 mg | Thirty 20 mg capsules; | 15 | 71881-124-01 | 71881-110-60
(Level 10) | Thirty 100 mg capsules |  | 71881-125-01
300 mg | Fifteen 300 mg sachets | 15 | 71881-111-01 | 71881-111-15
(Level 11)
Maintenance
300 mg | Thirty 300 mg sachets | 30 | 71881-111-01 | 71881-111-30
(Level 11)
NDC, National Drug Code.

Table 8: PALFORZIA Office Dose Kit Packaging Presentations
Packaging Presentation | Kit Components (Blisters, Capsules, or Sachets) | Number of Doses per Kit | NDC Numbers (Kit Components) | NDC Number (Kit)
3 mg | Eighteen blisters, each containing: | 18 | 71881-101-09 | 71881-101-99
(Level 1) | Three 1 mg capsules |  | 71881-122-01
6 mg | Eighteen blisters, each containing: | 18 | 71881-102-09 | 71881-102-99
(Level 2) | Six 1 mg capsules |  | 71881-122-01
12 mg | Twelve blisters, each containing: | 12 | 71881-103-09 | 71881-103-99
(Level 3) | Two 1 mg capsules |  | 71881-122-01
 | One 10 mg capsule |  | 71881-123-01
20 mg | Twelve blisters, each containing: | 12 | 71881-104-09 | 71881-104-99
(Level 4) | One 20 mg capsule |  | 71881-124-01
40 mg | Twelve blisters, each containing: | 12 | 71881-105-09 | 71881-105-99
(Level 5) | Two 20 mg capsules |  | 71881-124-01
80 mg | Twelve blisters, each containing: | 12 | 71881-106-09 | 71881-106-99
(Level 6) | Four 20 mg capsules |  | 71881-124-01
120 mg | Twelve blisters, each containing: | 12 | 71881-107-09 | 71881-107-99
(Level 7) | One 20 mg capsule |  | 71881-124-01
 | One 100 mg capsule |  | 71881-125-01
160 mg | Twelve blisters, each containing: | 12 | 71881-108-09 | 71881-108-99
(Level 8) | Three 20 mg capsules |  | 71881-124-01
 | One 100 mg capsule |  | 71881-125-01
200 mg | Twelve blisters, each containing: | 12 | 71881-109-09 | 71881-109-99
(Level 9) | Two 100 mg capsules |  | 71881-125-01
240 mg | Twelve blisters, each containing: | 12 | 71881-110-09 | 71881-110-99
(Level 10) | Two 20 mg capsules |  | 71881-124-01
 | Two 100 mg capsules |  | 71881-125-01
300 mg | Fifteen 300 mg sachets | 15 | 71881-111-09 | 71881-111-99
(Level 11)
NDC, National Drug Code.

STORAGE AND HANDLING

Store PALFORZIA at room temperature or in a refrigerator at 2° to 25°C (36° to 77°F). Avoid excessive heat. Do not freeze. Store in the original packaging until use to protect from moisture.

17 PATIENT COUNSELING INFORMATION

Advise patient, parent, or guardian to read the FDA-approved patient labeling (Medication Guide).

Advise patient, parent, or guardian that patient should follow a strict peanut-avoidant diet.

Advise patient, parent, or guardian that PALFORZIA will not mitigate allergic reactions to other foods to which they might be allergic.

Allergic Reactions

Advise patient, parent, or guardian that PALFORZIA may cause allergic reactions, including anaphylaxis that may be life-threatening. Educate patient, parent, or guardian to recognize the signs and symptoms of an allergic reaction [see Warnings and Precautions (5.1)] . The signs and symptoms of a severe allergic reaction may include syncope, dizziness, hypotension, tachycardia, dyspnea, wheezing, bronchospasm, chest discomfort, cough, abdominal pain, vomiting, diarrhea, rash, pruritus, flushing, and urticaria.

Ensure patient has injectable epinephrine and instruct patient, parent, or guardian on its proper use and that injectable epinephrine must be available for immediate use at all times. Instruct patient, parent, or guardian that if patient experiences a severe allergic reaction to seek immediate medical care, discontinue PALFORZIA, and resume treatment only when advised by their health care professional [see Warnings and Precautions (5.1)] .

Advise patient, parent, or guardian to read the patient information for epinephrine.

Inform patient, parent, or guardian that the first dose of each dose level of PALFORZIA must be administered in a health care setting under the supervision of a health care professional, and that after consuming PALFORZIA, patient will be monitored for signs and symptoms of an allergic reaction [see Warnings and Precautions (5.1)] .

Advise patient, parent, or guardian that if patient experiences an escalating or persistent allergic reaction or becomes intolerant to PALFORZIA at home to contact their health care professional immediately.

Administration of PALFORZIA to young patients should be under adult supervision [see Dosage and Administration (2)] .

PALFORZIA Risk Evaluation and Mitigation Strategy (REMS) Program

Advise patient that due to the risk of anaphylaxis, PALFORZIA is only available through a restricted program called the PALFORZIA REMS Program [see Warnings and Precautions (5.2)] .

Inform patient, parent, or guardian of the following requirements:

- Patient must be enrolled in the PALFORZIA REMS Program.
- Patient, parent or guardian must be educated on the need for monitoring with the Initial Dose Escalation and first dose of each Up-Dosing level and how to recognize the signs and symptoms of anaphylaxis.
- Patient must continue dietary peanut avoidance.
- Injectable epinephrine must be available to patient for immediate use at all times.

Asthma

Instruct patient, parent, or guardian that patients with asthma should stop taking PALFORZIA and contact their health care professional immediately if they have difficulty breathing or if their asthma becomes difficult to control [see Warnings and Precautions (5.3)] .

Eosinophilic Esophagitis

Because of the risk of eosinophilic esophagitis, instruct patient, parent or guardian that patients with severe or persistent symptoms of esophagitis or gastrointestinal intolerance should discontinue PALFORZIA and contact their health care professional [see Warnings and Precautions (5.4 and 5.5)] .

Handling Instructions

Advise patient, parent, or guardian of the following:

- To store PALFORZIA in a refrigerator.
- That patient must not swallow capsule(s) or inhale the powder.
- To open capsule(s) or sachet and empty the entire dose onto a few spoonfuls of refrigerated or room temperature semisolid food (e.g., applesauce, yogurt, pudding) and to mix well. Do not use liquid (e.g., milk, water, juice) to prepare PALFORZIA for consumption.
- That patient should consume the entire prepared mixture.
- To dispose of all unused PALFORZIA [see Dosage and Administration (2.3)].
- To dispose of the opened capsule(s) or sachet and wash hands immediately after handling.

Dosing Instructions

Advise patient, parent, or guardian of the following:

- The importance of taking each dose daily to avoid loss of treatment effect.
- That each dose should be consumed with a meal, at approximately the same time each day, preferably in the evening.
- To observe the patient for at least 60 minutes after administering PALFORZIA for any signs of intolerability.
- To contact their health care professional for advice on how to resume PALFORZIA if doses are missed.
- That the risk of an allergic reaction following PALFORZIA administration may be increased in the presence of cofactors such as:
  - Exercise or hot water exposure (e.g. a hypermetabolic state)
  - A medical event such as an intercurrent illness (e.g., viral infection)
  - Fasting
  - Menstruation
  - Sleep deprivation
  - Nonsteroidal anti-inflammatory drug use
  - Uncontrolled asthma
  Temporarily withholding or decreasing PALFORZIA doses may be required in the presence of these cofactors.

Patient should delay consuming PALFORZIA after strenuous exercise until signs of a hypermetabolic state (e.g., flushing, sweating, rapid breathing, rapid heart rate) have subsided and avoid taking hot showers or baths immediately prior to or within 3 hours after consuming PALFORZIA.

Manufactured by:
Aimmune Therapeutics, Inc.
Brisbane, CA 94005

© 2020 Aimmune Therapeutics, Inc.
PALFORZIA is a trademark of Aimmune Therapeutics, Inc.

US License No. 2109

PALF-US-v1.0

MEDICATION GUIDE
PALFORZIA
[Peanut (Arachis hypogaea) Allergen Powder-dnfp]
Powder for oral administration

Carefully read this Medication Guide before you start taking PALFORZIA and each time you receive a new dose level. This Medication Guide does not take the place of talking to your doctor about your medical condition or treatment. Talk with your doctor or pharmacist if there is something you do not understand, or you want to learn more about PALFORZIA.

What is the most important information I should know about PALFORZIA?
PALFORZIA can cause severe allergic reactions called anaphylaxis that may be life-threatening.

- You will receive your first dose in a healthcare setting under the observation of trained healthcare staff.
- You will receive the first dose of all dose increases in a healthcare setting.
- In the healthcare setting, you will be observed for at least 1 hour for signs and symptoms of a severe allergic reaction.
- If you have a severe reaction during treatment, you will need to receive an injection of epinephrine immediately and get emergency medical help right away.
- You will return to the healthcare setting for any trouble tolerating your home doses.

Stop taking PALFORZIA and get emergency medical treatment right away if you have any of the following symptoms after taking PALFORZIA:

- Trouble breathing or wheezing
- Chest discomfort or tightness
- Throat tightness
- Trouble swallowing or speaking
- Swelling of your face, lips, eyes, or tongue
- Dizziness or fainting
- Severe stomach cramps or pain, vomiting, or diarrhea
- Hives (itchy, raised bumps on skin)
- Severe flushing of the skin

For home administration of PALFORZIA, your doctor will prescribe injectable epinephrine, a medicine you must inject if you have a severe allergic reaction after taking PALFORZIA. Your doctor will train and instruct you on the proper use of injectable epinephrine.

Talk to your doctor and read the epinephrine patient information if you have any questions about the use of injectable epinephrine.

PALFORZIA is only available through a restricted program called the PALFORZIA Risk Evaluation and Mitigation Strategy (REMS) Program. Before you can receive PALFORZIA, you must:

- Enroll in this program.
- Receive education about the risk of a severe allergic reaction (anaphylaxis) by a healthcare provider who practices in a setting that is certified through the REMS program.
- Understand that you will be monitored in a healthcare setting during and after the Initial Dose Escalation and for the first dose of each Up-Dosing level (see Dosing Information).
- Receive education about how to maintain a peanut-free diet. You must attest that you will continue to avoid peanuts at all times.
- Fill the prescription your healthcare provider gives you for the injectable epinephrine. You must attest that epinephrine will be available to you at all times.

Talk to your healthcare provider for more information about the PALFORZIA REMS program and how to enroll.

What is PALFORZIA?
PALFORZIA is a prescription medicine derived from peanuts. It is a treatment for people who are allergic to peanuts. PALFORZIA can help reduce the severity of allergic reactions, including anaphylaxis, that may occur with accidental exposure to peanut. PALFORZIA may be started in patients aged 4 through 17 years old.
If you turn 18 years of age while on PALFORZIA treatment you should continue taking PALFORZIA unless otherwise instructed by your doctor.
PALFORZIA is intended to gradually decrease your sensitivity to small amounts of peanuts that may be hidden in foods.
PALFORZIA is a medication that must be taken daily to maintain the treatment effect.
PALFORZIA is only intended to treat people with peanut allergy; it is not effective against other food allergies you may have.
PALFORZIA does NOT treat allergic reactions and should not be given during an allergic reaction.
You must maintain a strict peanut-free diet while taking PALFORZIA.

Who should not take PALFORZIA?
You should NOT take PALFORZIA if:

- You have uncontrolled asthma.
- You ever had eosinophilic esophagitis (EoE) or other eosinophilic gastrointestinal disease.

What should I tell my doctor before taking PALFORZIA?
Tell your doctor if you are not feeling well prior to starting treatment with PALFORZIA. Your doctor may decide to delay treatment until you are feeling better. Also tell your doctor about any medical conditions you have. You should tell your doctor if you are taking or have recently taken any other medicines, including medicines obtained without a prescription and herbal supplements. Keep a list of them and show it to your doctor and pharmacist each time you get a new supply of PALFORZIA.
Tell your doctor if you are pregnant, planning to become pregnant, or breastfeeding.
Your doctor may decide that PALFORZIA is not the best treatment if:

- You are unwilling or unable to receive (or self-administer) injectable epinephrine.
- You have a condition or are taking a medication that reduces the ability to survive a severe allergic reaction.

Are there any reasons to stop taking PALFORZIA?
Stop taking PALFORZIA and contact your doctor immediately if you have a severe allergic reaction which may include any of the following symptoms:

- Throat tightness that worsens or swelling of the tongue or throat that causes trouble speaking, breathing, or swallowing
- Swelling of your face, lips, eyes, or tongue
- Asthma, wheezing, chest tightness, or any other breathing condition that gets worse
- Dizziness or fainting
- Severe stomach cramps or pain, vomiting, or diarrhea
- Severe flushing of the skin
- Hives (itchy, raised bumps on the skin)
- Heartburn, difficulty swallowing, pain with swallowing, or chest pain that does not go away or worsens

How should I take PALFORZIA?

Dosing Information

There are three different phases of dosing with PALFORZIA – Initial Dose Escalation, Up-Dosing, and Maintenance Dosing.
Initial Dose Escalation:
The first 5 doses (Initial Dose Escalation) of PALFORZIA will be administered on a single day in your doctor's office. If you do not tolerate the Initial Dose Escalation, your doctor may not continue your treatment with PALFORZIA.
Up-Dosing:
If you tolerate the Initial Dose Escalation phase, you will return to your doctor's office the next day to start the Up-Dosing phase. There are 11 different dose levels of Up-Dosing, starting with PALFORZIA 3 mg (Level 1) and finishing with PALFORZIA 300 mg (Level 11). The first dose of each Up-Dosing level is given in your doctor's office. If you tolerate the first dose of a new dose level, your doctor will ask you to continue to take that dose level every day at home. PALFORZIA should be taken at approximately the same time each day.
During Up-Dosing, you will return to your doctor's office approximately every 2 weeks to be assessed for a new Up-Dosing level. Dose levels cannot be skipped.
Maintenance Dosing:
If you tolerate all dose levels of the Up-Dosing phase, your doctor will ask you to continue taking PALFORZIA at a 300 mg dose every day as Maintenance therapy.
PALFORZIA must be taken every day for it to be effective.
Your doctor will tell you if you can take other medicines with PALFORZIA, such as other allergy treatments, medicines for your stomach, or medicines for any other conditions that you have.
Preparation of Product
Prepare and take PALFORZIA exactly as instructed by your doctor.
PALFORZIA is an oral powder that is mixed with refrigerated or room temperature soft food such as applesauce, yogurt, pudding, or other food.
PALFORZIA is provided as either capsules or sachets. PALFORZIA oral powder should be completely emptied from the capsules or sachets into the food before mixing.
Do not swallow the capsules.
Do not breathe in the powder. This could cause breathing problems (worsening of asthma) or cause an allergic reaction.
PALFORZIA must be stored in a refrigerator.
Open the daily dose of PALFORZIA capsule(s) or sachet and empty the full dose of PALFORZIA oral powder on to refrigerated or room temperature soft food such as applesauce, yogurt, or pudding. Do not use liquid (e.g., milk, water, juice) to prepare. Mix well.
The amount of food for mixing must enable you to take the full dose of PALFORZIA in a few spoonfuls.
You should take PALFORZIA immediately after mixing.
Wash your hands immediately after handling PALFORZIA capsules or sachets.
Additional Instructions
Take PALFORZIA at about the same time every day with a meal.
PALFORZIA must be taken every day in order to maintain the treatment effect.
Be aware that allergic reactions are more likely to develop within approximately 1 hour after taking PALFORZIA.
Do not take more than one dose of PALFORZIA in a single day.
Do not take PALFORZIA at home on the days that you visit your doctor for PALFORZIA Up Dosing as your doctor may give you PALFORZIA on these days.
If you miss taking PALFORZIA, contact your doctor. Do not take additional doses on the same day to make-up for missed doses.
Do not exercise or have a hot bath or shower within 3 hours after taking PALFORZIA.
If you have been exercising or have taken a hot bath or shower and are feeling hot, or you are sweating and your heart is beating fast, do not take PALFORZIA until you have cooled down and your heart is beating normally.
Certain conditions may increase the likelihood of an allergic reaction. These include:

- Having an illness such a viral infection
- Being very tired or missing sleep
- Being stressed
- Having your menstrual period
- Exercising
- Taking certain pain medications such as aspirin or ibuprofen
- Drinking alcohol

What are the possible side effects of PALFORZIA?
The most commonly reported side effects were: stomach pain, vomiting, feeling sick, itching or burning in the mouth, throat irritation, cough, runny nose, sneezing, throat tightness, wheezing, shortness of breath, itchy skin, hives, and/or itchy ears.
PALFORZIA can cause severe allergic reactions that may be life-threatening. Symptoms of allergic reactions to PALFORZIA can include:

- Trouble breathing or wheezing
- Chest discomfort or tightness
- Throat tightness or swelling
- Trouble swallowing or speaking
- Swelling of your face, lips, eyes, or tongue
- Dizziness or fainting
- Severe stomach cramps or pain, vomiting, or diarrhea
- Skin rash, itching, or raised bumps on skin
- Severe flushing of the skin

PALFORZIA can cause stomach or gut symptoms including inflammation of the esophagus (called eosinophilic esophagitis). Symptoms of eosinophilic esophagitis can include:

- Trouble swallowing
- Food stuck in throat
- Burning in chest, mouth, or throat
- Vomiting
- Regurgitation of undigested food
- Feeling sick

For additional information on the possible side effects of PALFORZIA, talk with your doctor or pharmacist. You may report side effects to the U.S. Food and Drug Administration (FDA) at 1-800-FDA-1088 or www.fda.gov/medwatch.

How should I store PALFORZIA?
Refrigerate PALFORZIA at 2°C to 8°C (36°F to 46°F), do not freeze. Store in the original packaging until use to protect from moisture.
Keep PALFORZIA out of the reach of children.
Throw away any unused PALFORZIA after the expiration date.

General information about PALFORZIA
Medicines are sometimes prescribed for purposes other than those listed in a Medication Guide. Do not use PALFORZIA for a condition for which it was not prescribed. Do not give PALFORZIA to other people, even if they have the same symptoms. It may harm them. This Medication Guide summarizes the most important information about PALFORZIA. If you would like more information, talk with your doctor. You can ask your doctor or pharmacist for information about PALFORZIA that was written for healthcare professionals. For more information, go to: www.PALFORZIA.com or call 1-844-PALFORZ (1-844-725-3679) (toll-free).
Pregnancy Registry: PALFORZIA has not been studied in women who are pregnant. Aimmune has a registry for women who become pregnant while on PALFORZIA. The purpose of the registry is to follow the health of the mother and her baby. You are encouraged to contact the registry as soon as you become aware of your pregnancy by calling 1-833-AIM-2KNO (1-833-246-2566) or ask your health care provider to contact the registry for you.

Manufactured by:

Aimmune Therapeutics

Brisbane, California 94005

© 2020 Aimmune Therapeutics, Inc.
PALFORZIA is a trademark of Aimmune Therapeutics, Inc.
PALF-US-v1.0
01/2020

This Medication Guide has been approved by the U.S. Food and Drug Administration.

PRINCIPAL DISPLAY PANEL - Kit Blister Pack - Initial Dose Escalation

NDC 71881-113-13

Peanut (Arachis hypogaea)
Allergen Powder-dnfp

Palforzia™ Powder for oral administration

Initial Dose Escalation

Contains:
Dose A | One 0.5 mg white capsule
Dose B | One 1 mg red capsule
Dose C | One 0.5 mg white capsule and
 | One 1 mg red capsule
Dose D | Three 1 mg red capsules
Dose E | Six 1 mg red capsules

Dispense with the enclosed medication guide.
For 4 though 17 years of age.
Contains Peanut.
Rx only
aimmune™
THERAPEUTICS

PRINCIPAL DISPLAY PANEL - Three 1 mg Capsule Dose Pack

NDC 71881-101-45

Peanut (Arachis hypogaea) Allergen Powder-dnfp
Palforzia™ Powder for oral administration

3 mg

LEVEL 1

Daily Dose Pack

Each daily dose contains 3 mg comprised
of three 1 mg red capsules.

Each daily dose pack contains 15 daily doses.

Dispense with the enclosed medication guide.

For 4 years of age and older.

Contains Peanut.

Rx only

aimmune™
THERAPEUTICS

PRINCIPAL DISPLAY PANEL - Six 1 mg Capsule Dose Pack

NDC 71881-102-90

Peanut (Arachis hypogaea) Allergen Powder-dnfp
Palforzia™ Powder for oral administration

6 mg

LEVEL 2

Daily Dose Pack

Each daily dose contains 6 mg comprised
of six 1 mg red capsules.

Each daily dose pack contains 15 daily doses.

Dispense with the enclosed medication guide.

For 4 years of age and older.

Contains Peanut.

Rx only

aimmune™
THERAPEUTICS

PRINCIPAL DISPLAY PANEL - Kit Dose Pack - 12 mg

NDC 71881-103-45

Peanut (Arachis hypogaea) Allergen Powder-dnfp
Palforzia™ Powder for oral administration

12 mg

LEVEL 3

Daily Dose Pack

Each daily dose contains 12 mg comprised
of two 1 mg red capsules and one 10 mg
blue capsule.

Each daily dose pack contains 15 daily doses.

Dispense with the enclosed medication guide.

For 4 years of age and older.

Contains Peanut.

Rx only

aimmune™
THERAPEUTICS

PRINCIPAL DISPLAY PANEL - One 20 mg Capsule Dose Pack

NDC 71881-104-15

Peanut (Arachis hypogaea) Allergen Powder-dnfp
Palforzia™ Powder for oral administration

20 mg

LEVEL 4

Daily Dose Pack

Each daily dose contains 20 mg comprised
of one 20 mg white capsule.

Each daily dose pack contains 15 daily doses.

Dispense with the enclosed medication guide.

For 4 years of age and older.

Contains Peanut.

Rx only

aimmune™
THERAPEUTICS

PRINCIPAL DISPLAY PANEL - Two 20 mg Capsule Dose Pack

NDC 71881-105-30

Peanut (Arachis hypogaea) Allergen Powder-dnfp
Palforzia™ Powder for oral administration

40 mg

LEVEL 5

Daily Dose Pack

Each daily dose contains 40 mg comprised
of two 20 mg white capsules.

Each daily dose pack contains 15 daily doses.

Dispense with the enclosed medication guide.

For 4 years of age and older.

Contains Peanut.

Rx only

aimmune™
THERAPEUTICS

PRINCIPAL DISPLAY PANEL - Four 20 mg Capsule Dose Pack

NDC 71881-106-60

Peanut (Arachis hypogaea) Allergen Powder-dnfp
Palforzia™ Powder for oral administration

80 mg

LEVEL 6

Daily Dose Pack

Each daily dose contains 80 mg comprised
of four 20 mg white capsules.

Each daily dose pack contains 15 daily doses.

Dispense with the enclosed medication guide.

For 4 years of age and older.

Contains Peanut.

Rx only

aimmune™
THERAPEUTICS

PRINCIPAL DISPLAY PANEL - Kit Dose Pack - 120 mg

NDC 71881-107-30

Peanut (Arachis hypogaea) Allergen Powder-dnfp
Palforzia™ Powder for oral administration

120 mg

LEVEL 7

Daily Dose Pack

Each daily dose contains 120 mg comprised
of one 20 mg white capsule and one 100 mg
red capsule.

Each daily dose pack contains 15 daily doses.

Dispense with the enclosed medication guide.

For 4 years of age and older.

Contains Peanut.

Rx only

aimmune™
THERAPEUTICS

PRINCIPAL DISPLAY PANEL - Kit Dose Pack - 160 mg

NDC 71881-108-60

Peanut (Arachis hypogaea) Allergen Powder-dnfp
Palforzia™ Powder for oral administration

160 mg

LEVEL 8

Daily Dose Pack

Each daily dose contains 160 mg comprised
of three 20 mg white capsules and one 100 mg
red capsule.

Each daily dose pack contains 15 daily doses.

Dispense with the enclosed medication guide.

For 4 years of age and older.

Contains Peanut.

Rx only

aimmune™
THERAPEUTICS

PRINCIPAL DISPLAY PANEL - Two 100 mg Capsule Dose Pack

NDC 71881-109-30

Peanut (Arachis hypogaea) Allergen Powder-dnfp
Palforzia™ Powder for oral administration

200 mg

LEVEL 9

Daily Dose Pack

Each daily dose contains 200 mg comprised
of two 100 mg red capsules.

Each daily dose pack contains 15 daily doses.

Dispense with the enclosed medication guide.

For 4 years of age and older.

Contains Peanut.

Rx only

aimmune™
THERAPEUTICS

PRINCIPAL DISPLAY PANEL - Kit Dose Pack - 240 mg

NDC 71881-110-60

Peanut (Arachis hypogaea) Allergen Powder-dnfp
Palforzia™ Powder for oral administration

240 mg

LEVEL 10

Daily Dose Pack

Each daily dose contains 240 mg comprised
of two 20 mg white capsules and two 100 mg
red capsules.

Each daily dose pack contains 15 daily doses.

Dispense with the enclosed medication guide.

For 4 years of age and older.

Contains Peanut.

Rx only

aimmune™
THERAPEUTICS

PRINCIPAL DISPLAY PANEL - 300 mg Sachet Carton

NDC 71881-111-15

300 mg
One 300 mg sachet

LEVEL 11

Peanut (Arachis hypogaea)
Allergen Powder-dnfp

Palforzia™ Powder for oral administration

Carton contains two extra doses, if needed.
For more detailed information see medication guide.

15 Single Doses